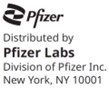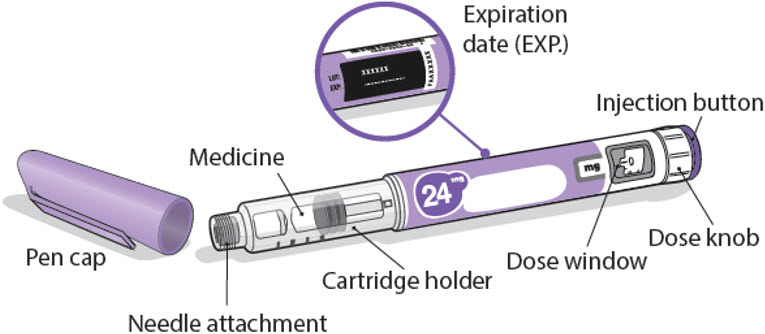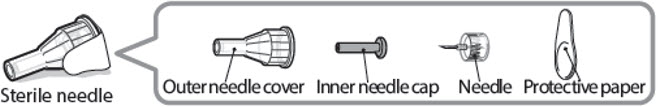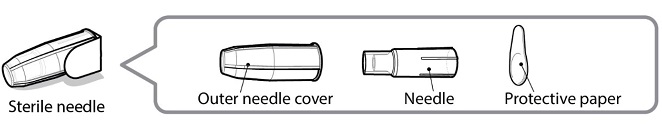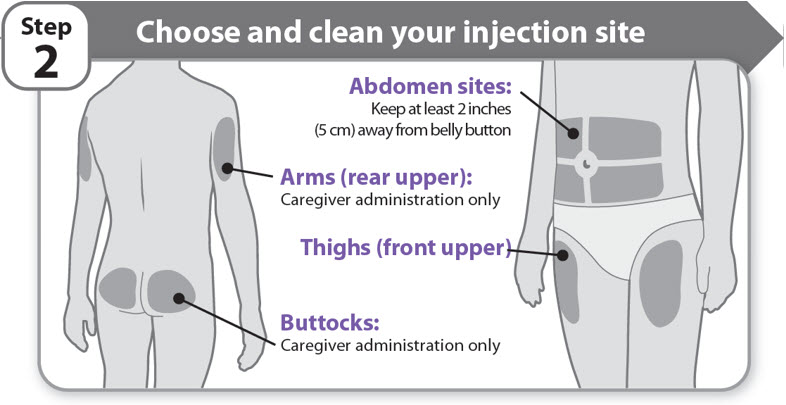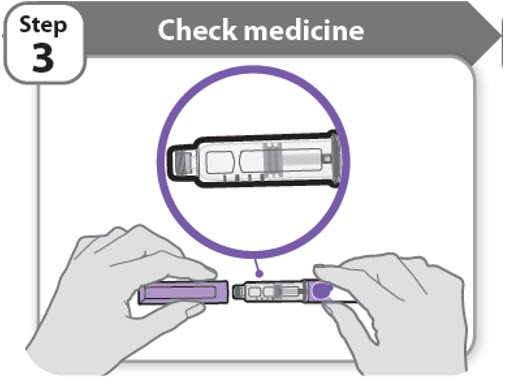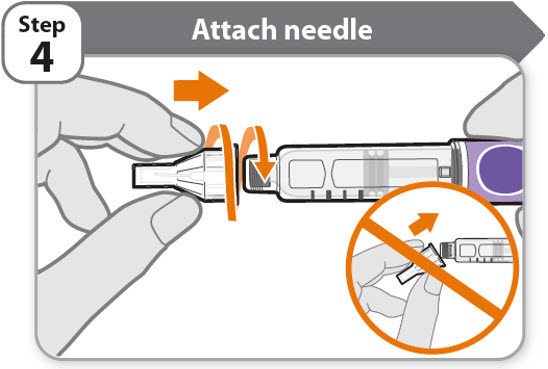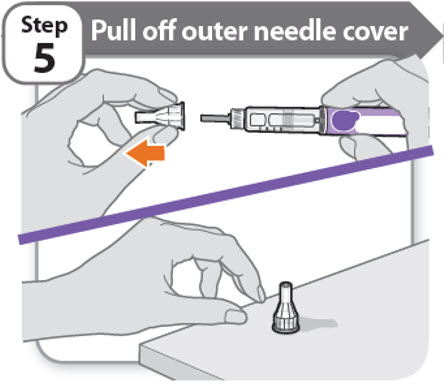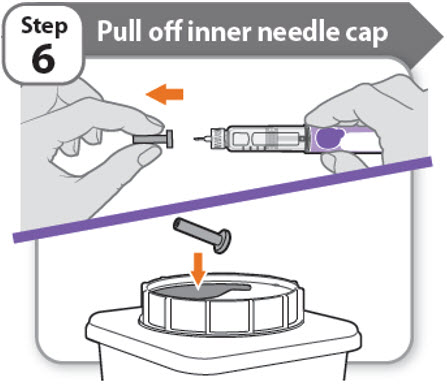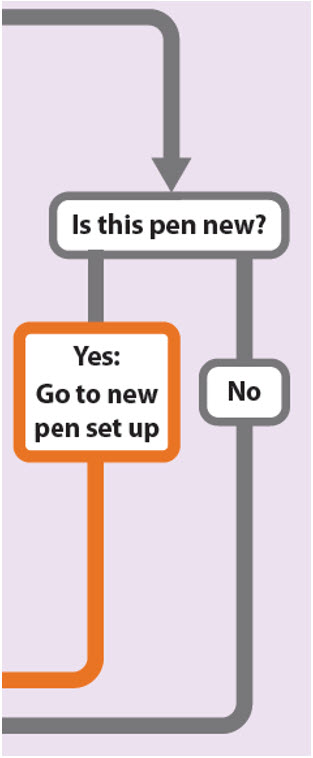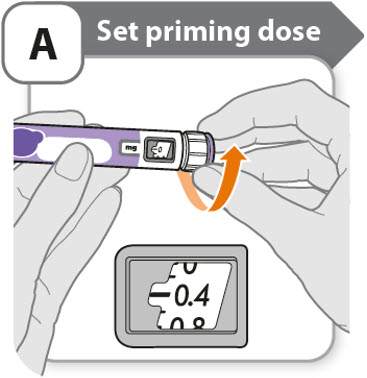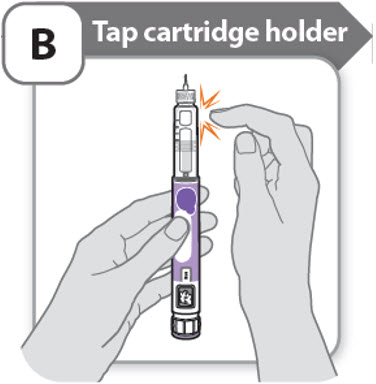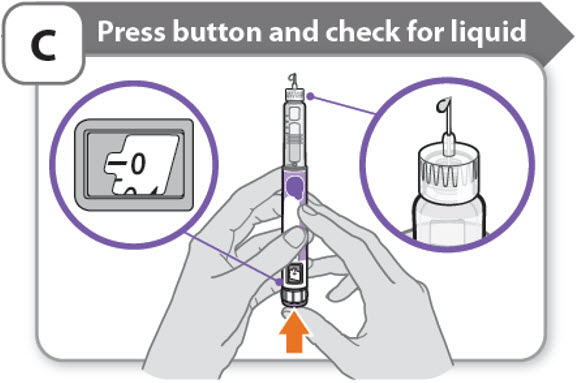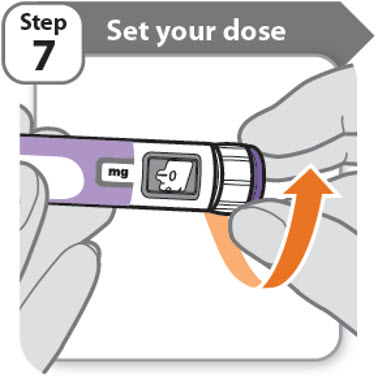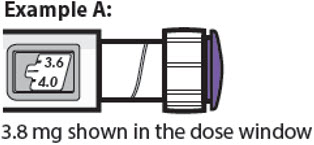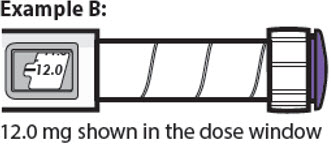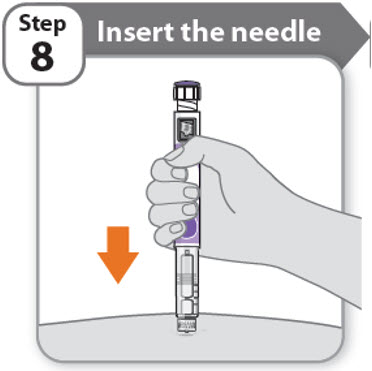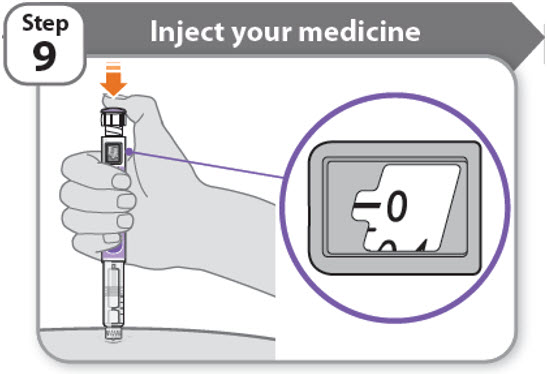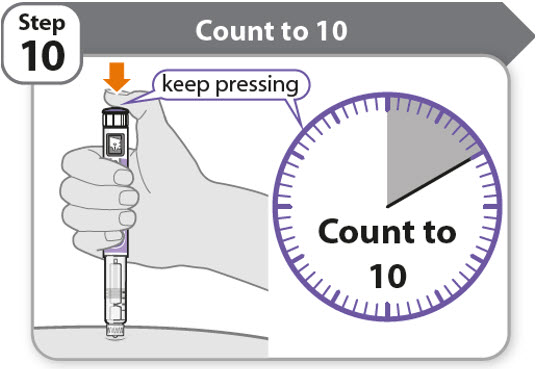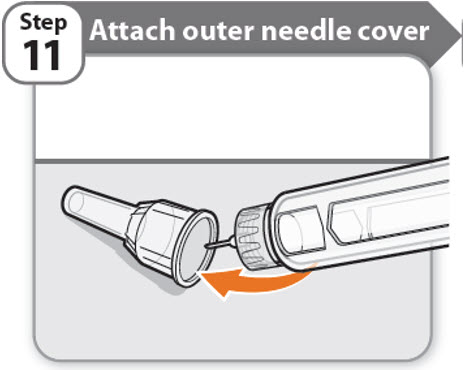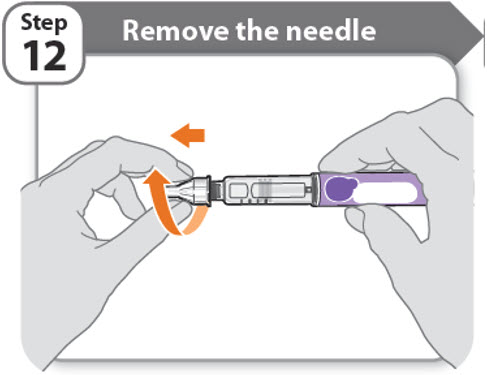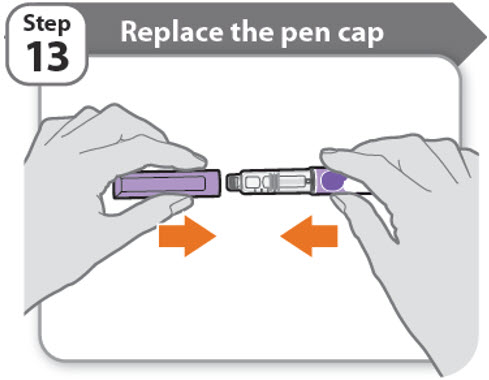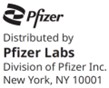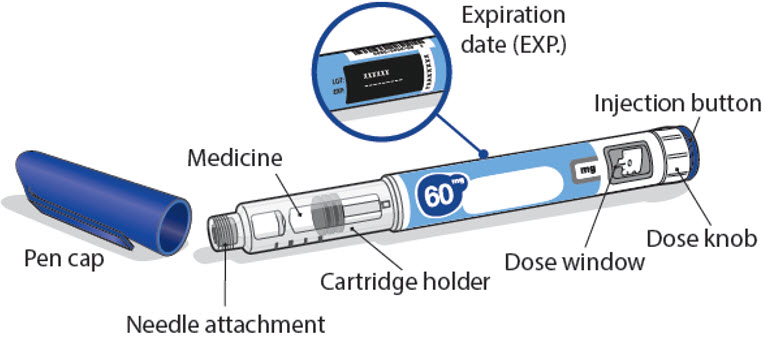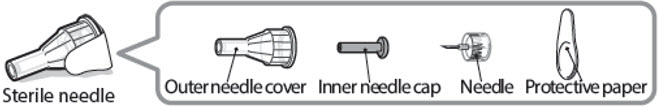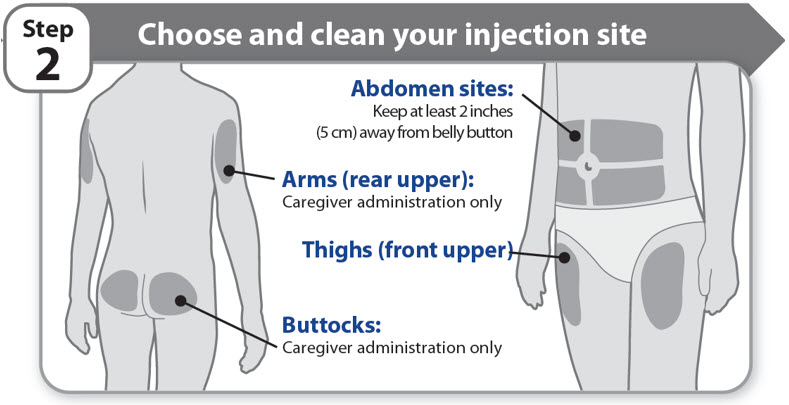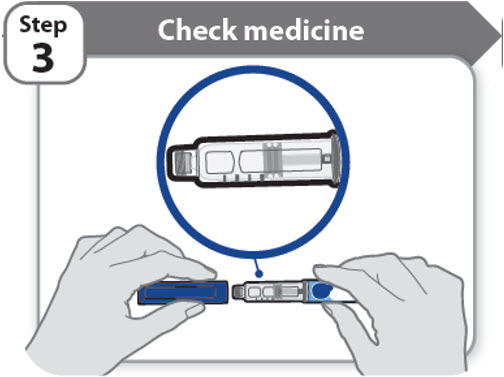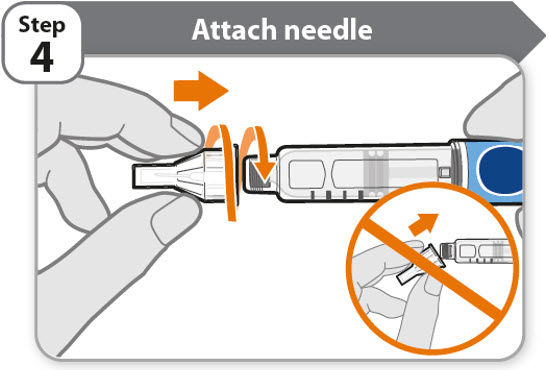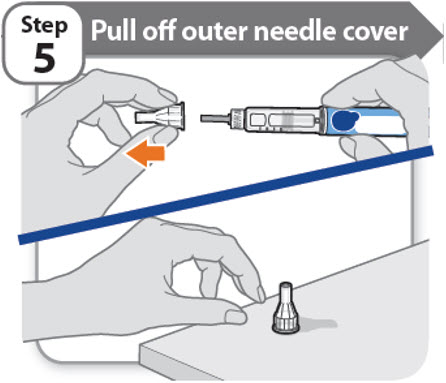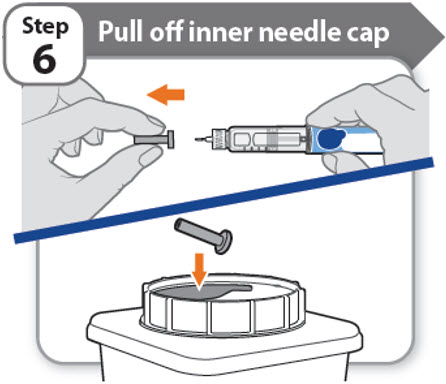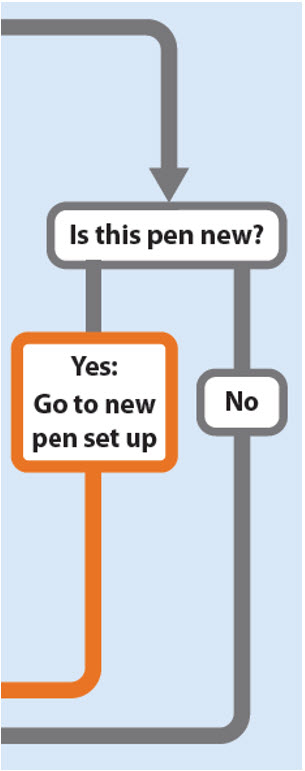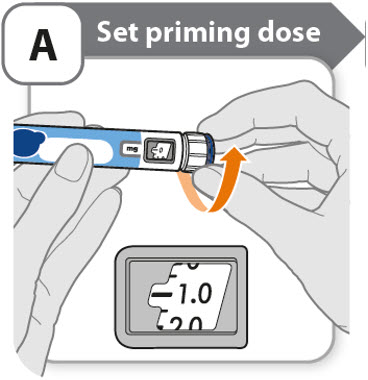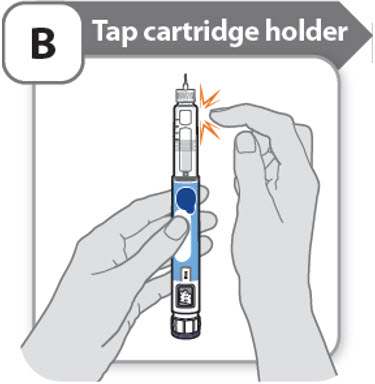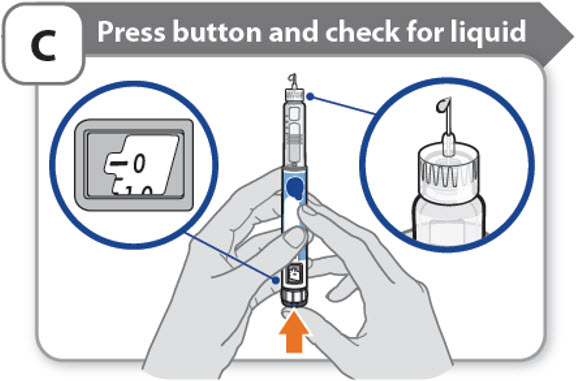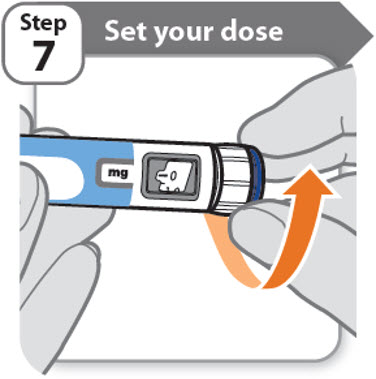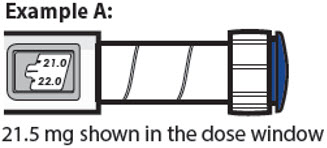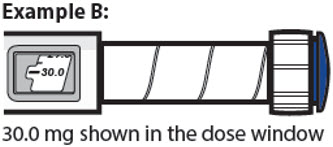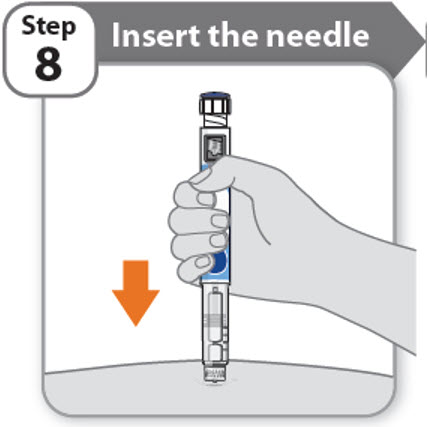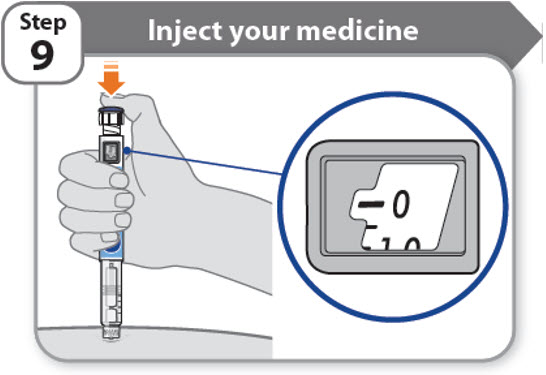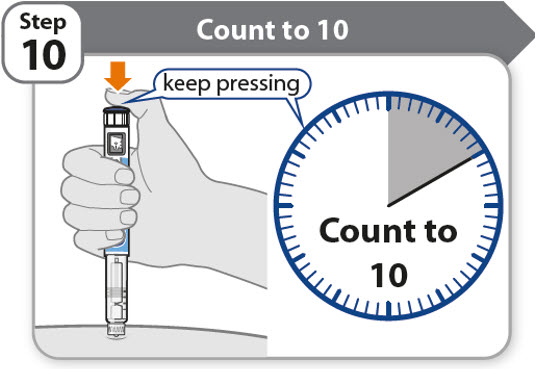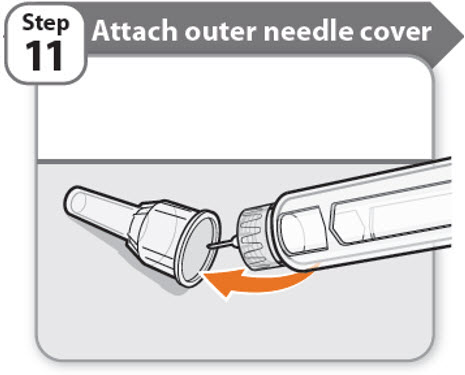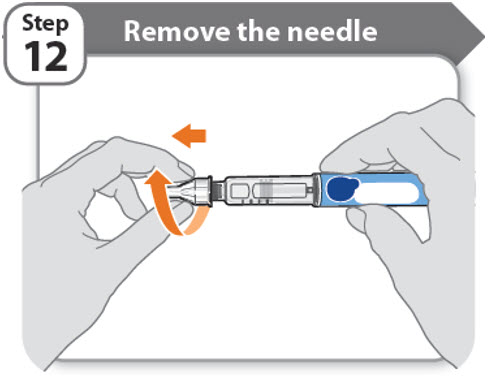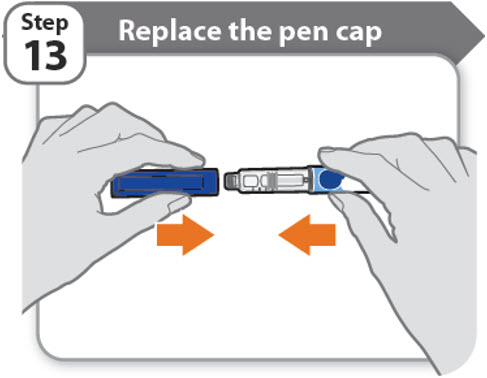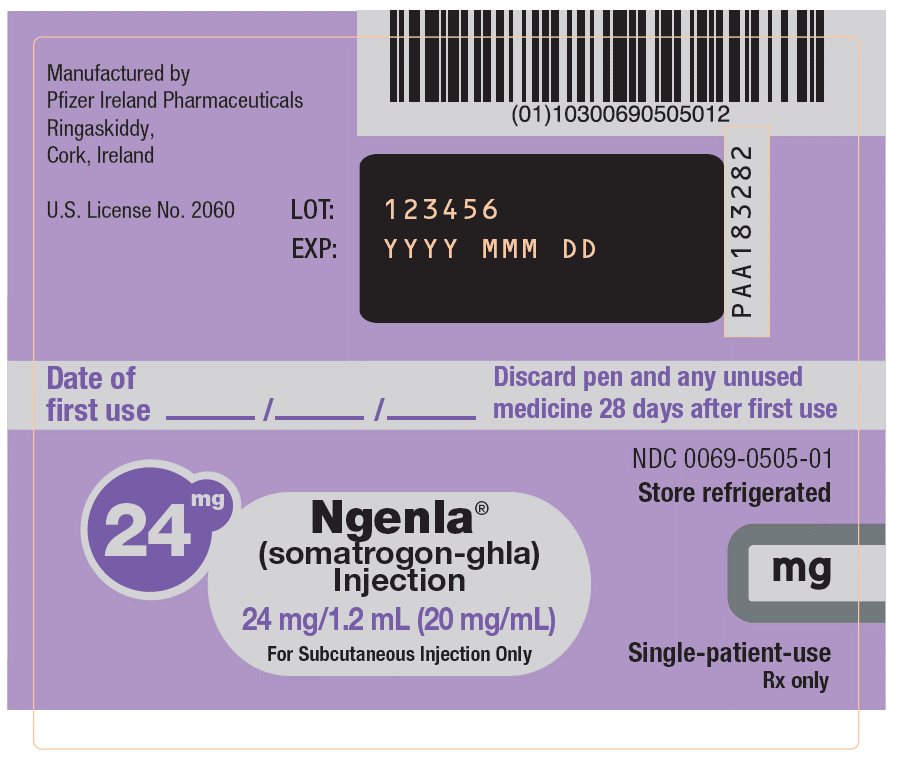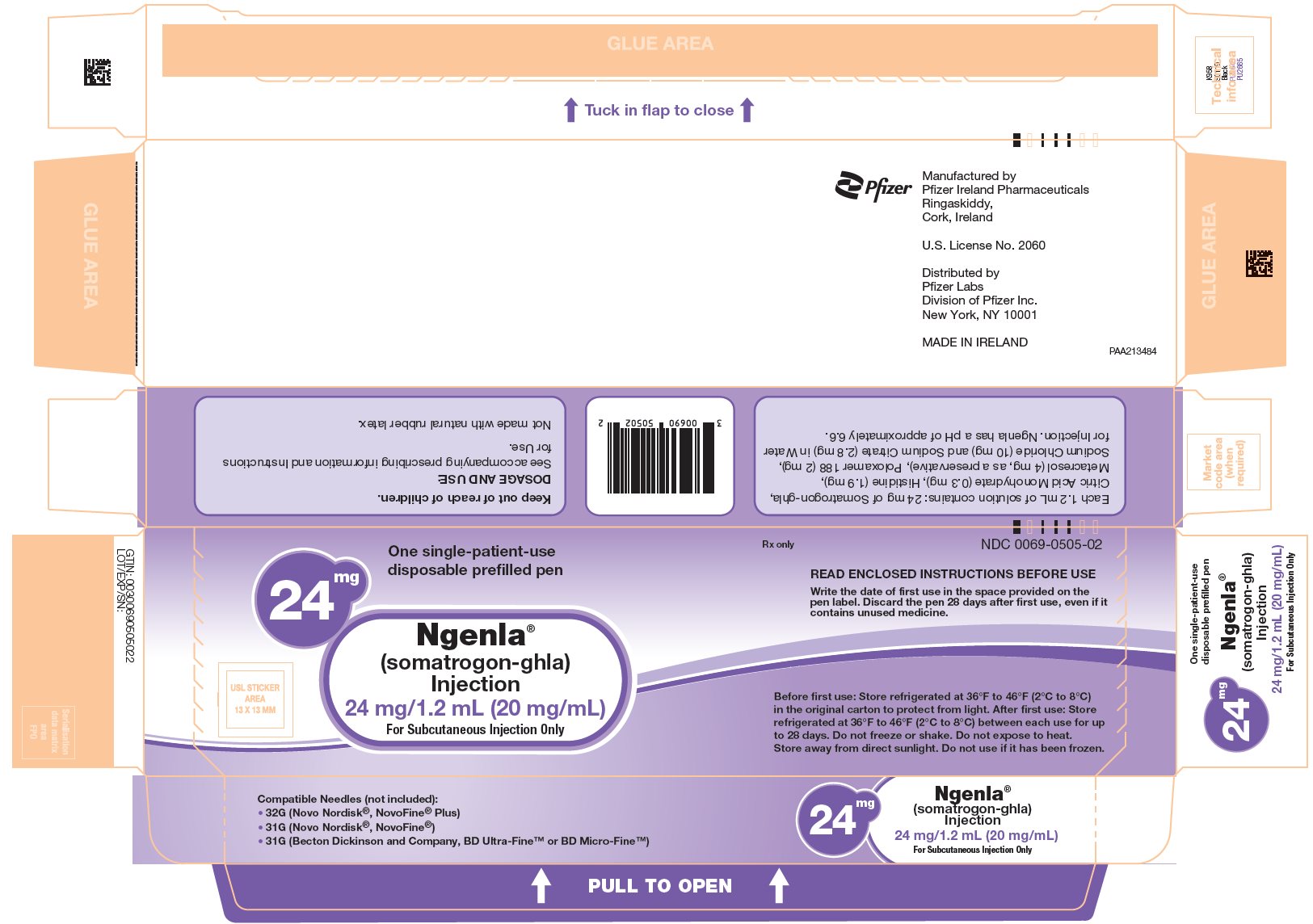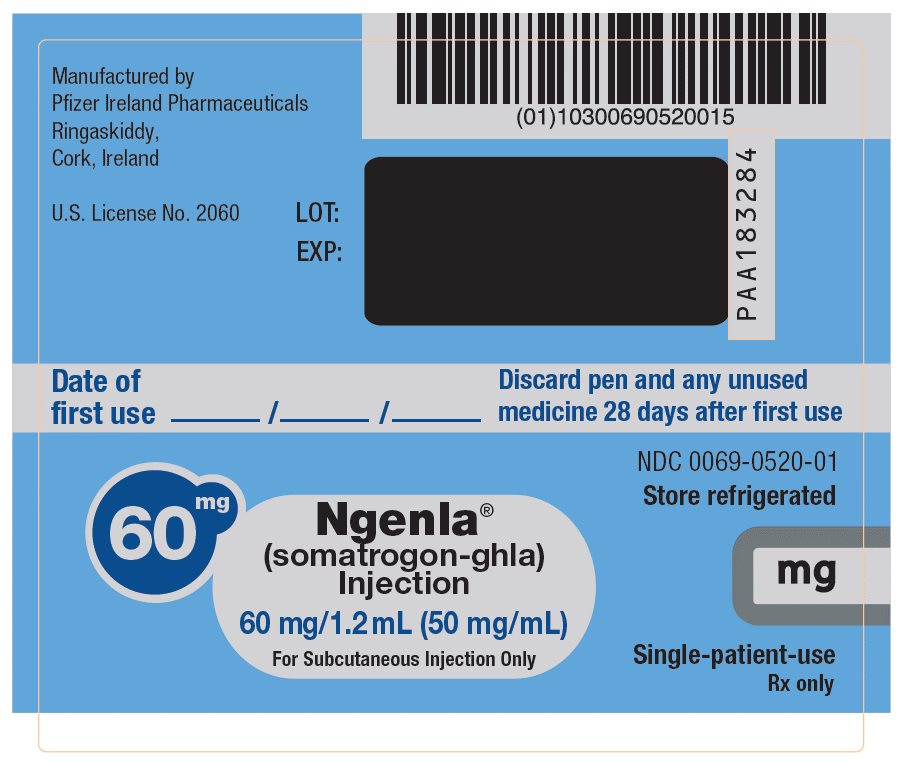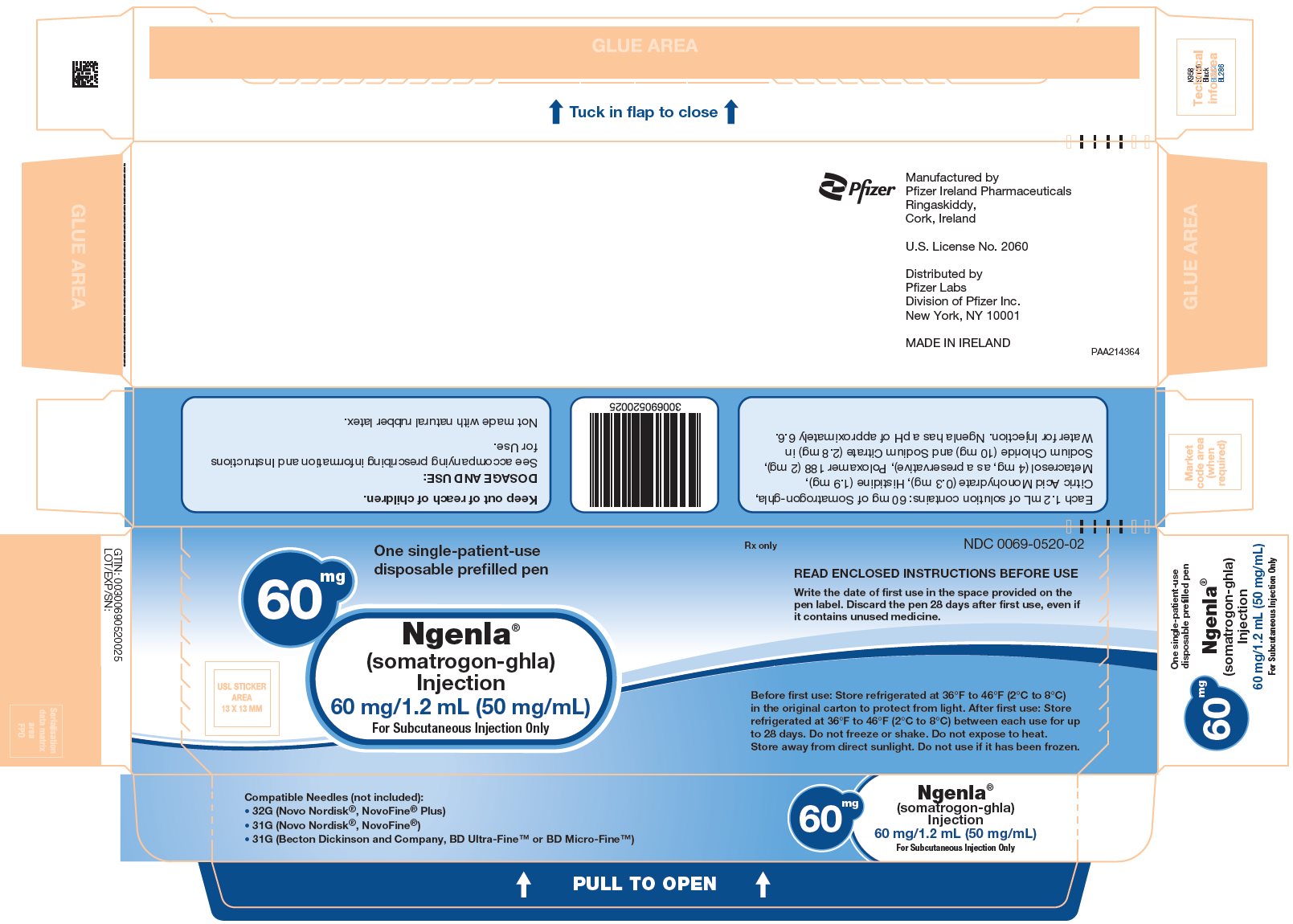 DRUG LABEL: Ngenla
NDC: 0069-0505 | Form: INJECTION, SOLUTION
Manufacturer: Pfizer Laboratories Div Pfizer Inc
Category: prescription | Type: HUMAN PRESCRIPTION DRUG LABEL
Date: 20250810

ACTIVE INGREDIENTS: SOMATROGON 24 mg/1.2 mL
INACTIVE INGREDIENTS: TRISODIUM CITRATE DIHYDRATE 3.1 mg/1.2 mL; CITRIC ACID MONOHYDRATE 0.3 mg/1.2 mL; HISTIDINE 1.9 mg/1.2 mL; SODIUM CHLORIDE 10 mg/1.2 mL; METACRESOL 4 mg/1.2 mL; POLOXAMER 188 2 mg/1.2 mL; WATER

HIGHLIGHTS OF PRESCRIBING INFORMATION

These highlights do not include all the information needed to use NGENLA safely and effectively. See full prescribing information for NGENLA.
NGENLA (somatrogon-ghla) injection, for subcutaneous use
Initial U.S. Approval: 2023

RECENT MAJOR CHANGES

Warnings and Precautions, Slipped Capital Femoral Epiphysis (5.9) | 07/2025

1 INDICATIONS AND USAGE

NGENLA is a human growth hormone analog indicated for treatment of pediatric patients aged 3 years and older who have growth failure due to inadequate secretion of endogenous growth hormone (1).

2 DOSAGE AND ADMINISTRATION

- NGENLA treatment should be supervised by a healthcare provider who is experienced in the diagnosis and management of pediatric patients with growth hormone deficiency (2.1).
- Administer NGENLA by subcutaneous injection once weekly, on the same day each week, at any time of the day in the abdomen, thighs, buttocks, or upper arms with weekly rotation of injection site (2.1).
- The recommended dosage is 0.66 mg/kg based on actual body weight administered once weekly (2.3).
- Individualize dosage for each patient based on the growth response (2.3).
- Patients switching from daily growth hormone may initiate treatment with once-weekly NGENLA on the day following their last daily injection (2.3).
- If more than one injection is required to deliver a complete dose, each injection should be administered at a different injection site (2.3).

3 DOSAGE FORMS AND STRENGTHS

Injection:

- 24 mg/1.2 mL (20 mg/mL) single-patient-use prefilled pen that delivers a dose in 0.2 mg increments (3).
- 60 mg/1.2 mL (50 mg/mL) single-patient-use prefilled pen that delivers a dose in 0.5 mg increments (3).

4 CONTRAINDICATIONS

- Acute critical illness (4).
- Hypersensitivity to somatrogon-ghla or excipients (4).
- Closed epiphyses (4).
- Active malignancy (4).
- Active proliferative or severe non-proliferative diabetic retinopathy (4).
- Prader-Willi syndrome who are severely obese or have severe respiratory impairment (4).

5 WARNINGS AND PRECAUTIONS

- Severe Hypersensitivity: Severe hypersensitivity reactions may occur. In the event of an allergic reaction, seek prompt medical attention (5.2).
- Increased Risk of Neoplasms: Monitor patients with preexisting tumors for progression or recurrence. Increased risk of a second neoplasm in childhood cancer survivors treated with somatropin – in particular meningiomas in patients treated with radiation to the head for their first neoplasm (5.3).
- Glucose Intolerance and Diabetes Mellitus: NGENLA may decrease insulin sensitivity, particularly at higher doses. Monitor glucose levels periodically in all patients receiving NGENLA, especially in patients with existing diabetes mellitus or at risk for its development (5.4).
- Intracranial Hypertension: Perform fundoscopic examinations prior to initiation of treatment with NGENLA and periodically thereafter. If preexisting papilledema is identified, evaluate the etiology and treat the underlying cause before initiating. If papilledema occurs with NGENLA, stop treatment (5.5).
- Fluid Retention: May occur and may be dose dependent. Reduce dose as necessary (5.6).
- Hypoadrenalism: Monitor patients for reduced serum cortisol levels and/or need for glucocorticoid dose increases in those with known hypoadrenalism (5.7).
- Hypothyroidism: Monitor thyroid function periodically as hypothyroidism may become evident or worsen after initiation with NGENLA (5.8).
- Slipped Capital Femoral Epiphysis: May develop. Evaluate patients with the onset of a limp or persistent hip or knee pain (5.9).
- Progression of Preexisting Scoliosis: Monitor for development or progression of scoliosis (5.10).
- Pancreatitis: Consider pancreatitis in patients with persistent severe abdominal pain (5.11).
- Lipoatrophy: May occur if NGENLA is administered in the same location over a long period of time. Rotate injection sites (5.12).

6 ADVERSE REACTIONS

Adverse reactions reported in ≥5% of patients treated with NGENLA are: injection site reactions, nasopharyngitis, headache, pyrexia, anemia, cough, vomiting, hypothyroidism, abdominal pain, rash, and oropharyngeal pain (6.1).
To report SUSPECTED ADVERSE REACTIONS, contact Pfizer Inc. at 1-800-438-1985 or FDA at 1-800-FDA-1088 or www.fda.gov/medwatch.

7 DRUG INTERACTIONS

- Replacement Glucocorticoid Treatment: Patients treated with glucocorticoid for hypoadrenalism may require an increase in their maintenance or stress dose following initiation of NGENLA (7).
- Pharmacologic Glucocorticoid Therapy and Supraphysiologic Glucocorticoid Treatment: Adjust glucocorticoid dosing in pediatric patients to avoid both hypoadrenalism and an inhibitory effect on growth (7).
- Cytochrome P450-Metabolized Drugs: NGENLA may alter the clearance. Monitor carefully if used with NGENLA (7).
- Oral Estrogen: Larger doses of NGENLA may be required (7).
- Insulin and/or Other Antihyperglycemic Agents: Dose adjustment of insulin or antihyperglycemic agent may be required (5.4, 7).

FULL PRESCRIBING INFORMATION

1 INDICATIONS AND USAGE

NGENLA is indicated for the treatment of pediatric patients aged 3 years and older who have growth failure due to an inadequate secretion of endogenous growth hormone.

2 DOSAGE AND ADMINISTRATION

2.1 Important Dosing and Administration Information

- NGENLA treatment should be supervised by a healthcare provider who is experienced in the diagnosis and management of pediatric patients aged 3 years and older with growth failure due to growth hormone deficiency (GHD) [see Indications and Usage (1)].
- Refer patient to the Instructions for Use for complete administration instructions.
- Administer NGENLA by subcutaneous injection, once weekly, on the same day each week, at any time of the day in the abdomen, thighs, buttocks, or upper arms. Rotate the injection site weekly.
- Parenteral drug products should be inspected visually for particulate matter and discoloration prior to administration, whenever solution and container permit. If flakes, particles or discoloration are observed, do not use the pen. Do not shake; shaking can damage the product.
- Prefilled pens deliver somatrogon-ghla in 0.2 mg or 0.5 mg increments.

2.2 Perform Fundoscopic Examination Prior to Initiation of NGENLA

- Perform fundoscopic examination before initiating treatment with NGENLA to exclude preexisting papilledema. If papilledema is identified, evaluate the etiology and treat the underlying cause before initiating treatment with NGENLA [see Warnings and Precautions (5.4)].

2.3 Recommended Dosage and Monitoring for Pediatric Patients with GHD

- Recommended dosage of NGENLA is 0.66 mg/kg based on actual body weight administered once weekly by subcutaneous (SC) injection.
- Individualize dosage for each patient based on the growth response.
- The day of weekly administration can be changed if necessary as long as the time between 2 doses is at least 3 days. After selecting a new dosing day, the once weekly dosing should be continued.
- When switching from daily growth hormone, the once-weekly NGENLA may be initiated on the day following their last daily injection.
- If more than one injection is required to deliver a complete dose, each injection should be administered at a different injection site.

2.4 Missed Dose

- If a dose is missed, administer NGENLA as soon as possible within 3 days after the missed dose.
- If more than 3 days have passed, skip the missed dose and administer the next dose on the regularly scheduled day.

3 DOSAGE FORMS AND STRENGTHS

NGENLA (somatrogon-ghla) is a clear and colorless to slightly light yellow solution available as:

- Injection: 24 mg/1.2 mL (20 mg/mL) in a single-patient-use, disposable prefilled pen that delivers a dose in 0.2 mg increments.
- Injection: 60 mg/1.2 mL (50 mg/mL) in a single-patient-use, disposable prefilled pen that delivers a dose in 0.5 mg increments.

4 CONTRAINDICATIONS

- Acute critical illness after open heart surgery, abdominal surgery or multiple accidental trauma, or those with acute respiratory failure due to the risk of increased mortality with somatropin [see Warnings and Precautions (5.1)].
- Hypersensitivity to somatrogon-ghla or any of the excipients in NGENLA [see Warnings and Precautions (5.2)].
- Closed epiphyses.
- Active malignancy due to the risk of malignancy progression [see Warnings and Precautions (5.3)].
- Active proliferative or severe non-proliferative diabetic retinopathy [see Warnings and Precautions (5.4)].
- Prader-Willi syndrome who are severely obese, have a history of upper airway obstruction or sleep apnea or have severe respiratory impairment due to the risk of sudden death [see Warnings and Precautions (5.13)].

5 WARNINGS AND PRECAUTIONS

5.1 Increased Mortality in Patients with Acute Critical Illness

Increased mortality in patients with acute critical illness due to complications following open heart surgery, abdominal surgery or multiple accidental trauma, or those with acute respiratory failure has been reported with somatropin [see Contraindications (4)]. The safety of continuing NGENLA treatment for the approved indication in patients who concurrently develop these illnesses has not been established.

5.2 Severe Hypersensitivity

Severe systemic hypersensitivity reactions including anaphylaxis and angioedema have been reported with somatropin. Inform patients and/or caregivers that such reactions are possible and that prompt medical attention should be sought if an allergic reaction occurs. NGENLA is contraindicated in patients with known hypersensitivity to somatrogon-ghla or any excipients in NGENLA [see Contraindications (4)].

5.3 Increased Risk of Neoplasms

Active Malignancy

There is an increased risk of malignancy progression with somatropin treatment in patients with active malignancy [see Contraindications (4)]. Any preexisting malignancy should be inactive, and its treatment should be completed prior to instituting therapy with NGENLA. Discontinue NGENLA if there is evidence of recurrent malignancy.

Risk of Second Neoplasm in Pediatric Patients

In childhood cancer survivors, who were treated with radiation to the brain/head for their first neoplasm and who developed subsequent GHD and were treated with somatropin, an increased risk of a second neoplasm has been reported. Intracranial tumors, in particular meningiomas, were the most common of these second neoplasms. Monitor all patients with a history of GHD secondary to an intracranial neoplasm while on NGENLA therapy for progression or recurrence of the tumor.

New Malignancy During Treatment

Because children with certain rare genetic causes of short stature have an increased risk of developing malignancies, thoroughly consider the risks and benefits of starting NGENLA in these patients. If treatment with NGENLA is initiated, carefully monitor these patients for development of neoplasms.

Monitor patients on NGENLA therapy carefully for increased growth or potential malignant changes of preexisting nevi. Advise patients and/or caregivers to report marked changes in behavior, onset of headaches, vision disturbances and/or changes in skin pigmentation or changes in the appearance of preexisting nevi.

5.4 Glucose Intolerance and Diabetes Mellitus

Treatment with growth hormone may decrease insulin sensitivity, particularly at higher doses. New onset type 2 diabetes mellitus has been reported in patients receiving growth hormone. Patients with undiagnosed pre-diabetes and diabetes mellitus may experience worsened glycemic control and become symptomatic. Monitor glucose levels periodically in all patients receiving NGENLA, especially in those with risk factors for diabetes mellitus, such as obesity, Turner syndrome, or a family history of diabetes mellitus. Patients with preexisting type 1 or type 2 diabetes mellitus or pre-diabetes should be monitored closely. The doses of antidiabetic agents may require adjustment when NGENLA is initiated.

5.5 Intracranial Hypertension

Intracranial hypertension (IH) with papilledema, visual changes, headache, nausea, and/or vomiting has been reported in patients treated with somatropin. Symptoms usually occurred within the first eight (8) weeks after the initiation of somatropin therapy. In all reported cases, IH-associated signs and symptoms rapidly resolved after cessation of therapy or a reduction of somatropin dose.

Perform fundoscopic examination before initiating treatment with NGENLA to exclude preexisting papilledema and periodically thereafter. If papilledema is identified prior to initiation, evaluate the etiology and treat the underlying cause before initiating NGENLA. NGENLA should be temporarily discontinued in patients with clinical or fundoscopic evidence of IH. If IH is confirmed, restart treatment with NGENLA at a lower dose after IH-associated signs and symptoms have resolved.

5.6 Fluid Retention

Fluid retention during NGENLA therapy may occur. Clinical manifestations of fluid retention (e.g. edema and nerve compression syndromes including carpal tunnel syndrome/paresthesia) are usually transient and dose dependent.

5.7 Hypoadrenalism

Patients receiving growth hormone therapy who have or are at risk for pituitary hormone deficiency(s) may be at risk for reduced serum cortisol levels and/or unmasking of central (secondary) hypoadrenalism. In addition, patients treated with glucocorticoid replacement for previously diagnosed hypoadrenalism may require an increase in their maintenance or stress doses following initiation of NGENLA treatment. Monitor patients for reduced serum cortisol levels and/or need for glucocorticoid dose increases in those with known hypoadrenalism [see Drug Interactions (7)].

5.8 Hypothyroidism

Undiagnosed/untreated hypothyroidism may prevent an optimal response to NGENLA therapy. In patients with GH deficiency, central (secondary) hypothyroidism may first become evident or worsen during treatment with growth hormone therapy. Therefore, patients should have periodic thyroid function tests and thyroid hormone replacement therapy should be initiated or appropriately adjusted when indicated.

5.9 Slipped Capital Femoral Epiphysis

Slipped capital femoral epiphysis may occur more frequently in patients undergoing rapid growth. Slipped capital femoral epiphysis may lead to osteonecrosis. Cases of slipped capital femoral epiphysis with or without osteonecrosis have been reported in pediatric patients with short stature receiving somatropin. Evaluate pediatric patients receiving NGENLA with the onset of a limp or complaints of persistent hip or knee pain for slipped capital femoral epiphysis and osteonecrosis and manage accordingly.

5.10 Progression of Preexisting Scoliosis

NGENLA increases growth rate, and progression of preexisting scoliosis can occur in patients who experience rapid growth. Growth hormone treatment has not been shown to increase the occurrence of scoliosis. Monitor patients with a history of scoliosis for disease progression.

5.11 Pancreatitis

Cases of pancreatitis have been reported in patients receiving somatropin. The risk may be greater in pediatric patients compared with adults. Consider pancreatitis in patients who develop persistent severe abdominal pain.

5.12 Lipoatrophy

When NGENLA is administered subcutaneously at the same site over a long period of time, lipoatrophy may result. Rotate injection sites when administering NGENLA to reduce this risk [see Dosage and Administration (2.1)].

5.13 Sudden Death in Pediatric Patients with Prader-Willi Syndrome

There have been reports of sudden death after initiating therapy with somatropin in pediatric patients with Prader-Willi syndrome who had one or more of the following risk factors: severe obesity, history of upper airway obstruction or sleep apnea, or unidentified respiratory infection. Male patients with one or more of these factors may be at greater risk than females. NGENLA is not indicated for the treatment of pediatric patients who have growth failure due to genetically confirmed Prader-Willi syndrome.

5.14 Laboratory Tests

Serum levels of phosphorus, alkaline phosphatase, and parathyroid hormone may increase with NGENLA therapy. If a patient is found to have abnormal laboratory tests, monitor as appropriate.

6 ADVERSE REACTIONS

The following clinically significant adverse reactions are described elsewhere in the labeling:

- Increased mortality in patients with acute critical illness [see Warnings and Precautions (5.1)]
- Severe hypersensitivity [see Warnings and Precautions (5.2)]
- Increased risk of neoplasm [see Warnings and Precautions (5.3)]
- Glucose intolerance and diabetes mellitus [see Warnings and Precautions (5.4)]
- Intracranial hypertension [see Warnings and Precautions (5.5)]
- Fluid retention [see Warnings and Precautions (5.6)]
- Hypoadrenalism [see Warnings and Precautions (5.7)]
- Hypothyroidism [see Warnings and Precautions (5.8)]
- Slipped capital femoral epiphysis [see Warnings and Precautions (5.9)]
- Progression of preexisting scoliosis [see Warnings and Precautions (5.10)]
- Pancreatitis [see Warnings and Precautions (5.11)]
- Lipoatrophy [see Warnings and Precautions (5.12)]
- Sudden death in pediatric patients with Prader-Willi syndrome [see Warnings and Precautions (5.13)]

6.1 Clinical Trials Experience

Because clinical trials are conducted under widely varying conditions, adverse reaction rates observed in the clinical trials of a drug cannot be directly compared to rates in the clinical trials of another drug and may not reflect the rates observed in practice.

Safety data are derived from a safety and efficacy study in pediatric patients with GHD [see Clinical Studies (14.1)]. The data from the 12-month main study period reflect exposure of 109 patients to NGENLA administered once weekly (0.66 mg/kg/wk) and 115 patients to somatropin administered once daily (0.034 mg/kg/day).

The mean age across the treatment groups, was 7.7 years (min 3.01, max 11.96); 40.2% of patients were >3 years to ≤7 years, 59.8% were >7 years, 71.9% of patients were male, and 28.1% were female. In this study, 74.6% of patients were White, 20.1% were Asian, 0.9% were Black or African American, 0.5% were American Indian or Alaska Native, 0.5% were Native Hawaiian or Other Pacific Islander, and for 3.6% race information was missing; 10.7% of patients identified as Hispanic or Latino. Baseline disease characteristics were balanced across treatment groups.

Table 1 shows the adverse reactions that occurred in ≥5% of patients treated with NGENLA or daily somatropin during the 12-month main study period. Reporting of injection site reactions was solicited through the use of a patient diary after each weekly injection for patients administered NGENLA and once weekly for patients administered daily injections of somatropin.

Table 1 Adverse Reactions Occurring in ≥5% of NGENLA- or Somatropin-Treated Pediatric Patients (52 Weeks of Treatment)
Adverse Drug Reactions | Daily Somatropin; (N=115); n (%) | NGENLA; (N=109); n (%)
Injection site reactions [Injection site reactions included: injection site pain (39% somatrogon-ghla vs 25% daily somatropin), injection site swelling/induration/hypertrophy/inflammation (10% somatrogon-ghla vs 1% daily somatropin), injection site erythema (8% somatrogon-ghla vs none daily somatropin), injection site pruritus (5% somatrogon-ghla vs none daily somatropin), injection site hemorrhage (5% somatrogon-ghla vs none daily somatropin).] | 29 (25.2) | 46 (42.2)
Nasopharyngitis [Nasopharyngitis included: rhinitis, pharyngitis, rhinitis allergic, pharyngitis streptococcal, viral pharyngitis, nasopharyngitis.] | 33 (28.7) | 36 (33)
Headache | 25 (21.7) | 18 (16.5)
Pyrexia | 17 (14.8) | 18 (16.5)
Anemia | 10 (8.7) | 10 (9.2)
Cough | 9 (7.8) | 9 (8.3)
Vomiting | 9 (7.8) | 8 (7.3)
Hypothyroidism | 3 (2.6) | 7 (6.4)
Abdominal pain | 8 (7.0) | 7 (6.4)
Rash | 7 (6.1) | 6 (5.5)
Oropharyngeal pain | 4 (3.5) | 6 (5.5)
Arthralgia | 8 (7.0) | 5 (4.6)
Otitis media | 10 (8.7) | 5 (4.6)
Tonsillitis | 6 (5.2) | 5 (4.6)
Bronchitis | 9 (7.8) | 3 (2.8)
Adverse reactions that are medically related were grouped to a single preferred term.

Laboratory Tests

More NGENLA-treated patients shifted from normal eosinophil levels at baseline to elevated eosinophil levels at the end of the 12-month study compared to the daily somatropin group (29% vs 12%).

6.2 Postmarketing Experience

The following adverse reactions have been identified during post-approval use of somatropin. Because these reactions are reported voluntarily from a population of uncertain size, it is not always possible to reliably estimate their frequency or establish a causal relationship to drug exposure.

Musculoskeletal and connective tissue disorders – osteonecrosis in pediatric patients

7 DRUG INTERACTIONS

Table 2 includes a list of drugs with clinically significant drug interactions when administered concomitantly with NGENLA and instructions for preventing or managing them.

Table 2 Clinically Significant Drug Interactions with NGENLA
Replacement Glucocorticoid Treatment
Clinical Impact: | Microsomal enzyme 11β-hydroxysteroid dehydrogenase type 1 (11βHSD-1) is required for conversion of cortisone to its active metabolite, cortisol, in hepatic and adipose tissue. Growth hormone inhibits 11βHSD-1. Consequently, individuals with untreated GH deficiency have relative increases in 11βHSD-1 and serum cortisol. Initiation of NGENLA may result in inhibition of 11βHSD-1 and reduced serum cortisol concentrations.
Intervention: | Patients treated with glucocorticoid replacement for hypoadrenalism may require an increase in their maintenance or stress doses following initiation of NGENLA [see Warnings and Precautions (5.7)].
Examples: | Cortisone acetate and prednisone may be affected more than others because conversion of these drugs to their biologically active metabolites is dependent on the activity of 11βHSD-1.
Supraphysiologic Glucocorticoid Treatment
Clinical Impact: | Supraphysiologic glucocorticoid treatment may attenuate the growth-promoting effects of NGENLA in pediatric patients.
Intervention: | Carefully adjust glucocorticoid replacement dosing in pediatric patients receiving glucocorticoid treatments to avoid hypoadrenalism and an inhibitory effect on growth.
Cytochrome P450-Metabolized Drugs
Clinical Impact: | Limited published data indicate that growth hormone treatment increases cytochrome P450 (CYP450)-mediated antipyrine clearance. NGENLA may alter the clearance of compounds known to be metabolized by CYP450 liver enzymes.
Intervention: | Careful monitoring is advisable when NGENLA is administered in combination with drugs metabolized by CYP450 liver enzymes.
Oral Estrogen
Clinical Impact: | Oral estrogens may reduce the serum IGF-1 response to NGENLA.
Intervention: | Patients receiving oral estrogen replacement may require higher NGENLA dosages.
Insulin and/or Other Antihyperglycemic Agents
Clinical Impact: | Treatment with NGENLA may decrease insulin sensitivity, particularly at higher doses.
Intervention: | Patients with diabetes mellitus may require adjustment of their doses of insulin and/or other antihyperglycemic agents [see Warnings and Precautions (5.4)].

8 USE IN SPECIFIC POPULATIONS

8.1 Pregnancy

Risk Summary

There are no available data on NGENLA use in pregnant women to evaluate for a drug associated risk of major birth defects, miscarriage, or other adverse maternal or fetal outcomes. In reproduction studies with pregnant rats, there was no evidence of embryo-fetal toxicity following administration of somatrogon-ghla subcutaneously during organogenesis at doses up to 45 times the maximum recommended human dose based on exposure (see Data).

The background risk of major birth defects and miscarriage in the indicated population is unknown. In the U.S. general population, the estimated background risk of major birth defects and miscarriage in clinically recognized pregnancies is 2% to 4% and 15% to 20%, respectively.

Data

Animal Data

In an embryo-fetal development toxicity study in rats, no adverse maternal or embryo-fetal effects were observed when somatrogon-ghla was administered via subcutaneous injection every 2 days from gestation day (GD) 6 to 18 at doses up to 30 mg/kg (45 times the maximum recommended human dose based on Cav exposure).

In a pre- and postnatal development study in rats, somatrogon-ghla was administered via subcutaneous injection to pregnant rats every 2 days from GD 6 to lactation day 20 at doses up to 30 mg/kg. There was no evidence of maternal toxicity and no adverse effects on the first generation (F1) offspring. Somatrogon-ghla elicited an increase in F1 mean body weights in both sexes and increased the mean copulatory interval in F1 females at the highest dose (30 mg/kg), consistent with a longer estrous cycle length. However, there were no effects on mating indices in F1 females.

8.2 Lactation

Risk Summary

There are no data on the presence of somatrogon-ghla in human or animal milk, the effects on the breastfed infant, or the effects on milk production. The developmental and health benefits of breastfeeding should be considered along with the mother’s clinical need for NGENLA and any potential adverse effects on the breastfed infant from NGENLA or from the underlying maternal condition.

8.3 Females and Males of Reproductive Potential

Pregnancy Testing

Although somatrogon-ghla did not interfere with hCG pregnancy testing in a limited number of commercial tests, interference with hCG blood and urine pregnancy testing in patients receiving somatrogon-ghla may be possible, leading to either false positive or false negative results. Alternative methods (i.e., not reliant on hCG) are recommended to determine pregnancy.

8.4 Pediatric Use

The safety and effectiveness of NGENLA have been established for the treatment of growth failure due to inadequate secretion of endogenous growth hormone (GH) in pediatric patients aged 3 years and older [see Clinical Studies (14.1)]. The use of NGENLA for this indication is supported by evidence from a 52‑week, multi-center, randomized, open-label, active-controlled, parallel-group phase 3 study in 224 treatment-naïve, prepubertal pediatric subjects with growth hormone deficiency.

Risks in pediatric patients associated with growth hormone use include:

- Increased risk of second neoplasm in pediatric cancer survivors treated with radiation to the brain and/or head [see Warnings and Precautions (5.3)]
- Slipped capital femoral epiphysis [see Warnings and Precautions (5.9)]
- Progression of preexisting scoliosis [see Warnings and Precautions (5.10)]
- Pancreatitis [see Warnings and Precautions (5.11)]
- Sudden death in pediatric patients with Prader-Willi Syndrome. NGENLA is not indicated for the treatment of pediatric patients with growth failure secondary to genetically confirmed Prader‑Willi syndrome. [see Warnings and Precautions (5.13)]

10 OVERDOSAGE

Acute overdosage may lead initially to hypoglycemia and subsequently to hyperglycemia. Overdose with growth hormone may cause fluid retention. Long-term overdosage could result in signs and symptoms of gigantism consistent with the effects of excess growth hormone.

11 DESCRIPTION

Somatrogon-ghla, a human growth hormone analog, is a fusion protein produced in Chinese Hamster Ovary (CHO) cells by recombinant DNA technology. It is comprised of the amino acid sequence of human growth hormone (hGH) with one copy of the C-terminal peptide (CTP) from the beta chain of human chorionic gonadotropin (hCG) at the N-terminus and 2 copies of CTP (in tandem) at the C-terminus. Somatrogon-ghla has an approximate molecular weight of 40 KDa.

NGENLA (somatrogon-ghla) injection is a sterile, clear and colorless to slightly light yellow solution for subcutaneous use supplied in a 24 mg/1.2 mL (20 mg/mL) or 60 mg/1.2 mL (50 mg/mL) single-patient-use prefilled pen.

Each 1.2 mL of solution contains either 24 mg or 60 mg of somatrogon-ghla, and the inactive ingredients citric acid monohydrate (0.3 mg), histidine (1.9 mg), metacresol (4 mg, as a preservative), poloxamer 188 (2 mg), sodium chloride (10 mg) and sodium citrate (2.8 mg) in water for injection. NGENLA has a pH of approximately 6.6.

12 CLINICAL PHARMACOLOGY

12.1 Mechanism of Action

Somatrogon-ghla binds to the GH receptor and initiates a signal transduction cascade culminating in changes in growth and metabolism. Somatrogon-ghla binding leads to activation of the STAT5b signaling pathway and increases the serum concentration of Insulin-like Growth Factor (IGF-1). GH and IGF-1 stimulate metabolic changes, linear growth, and enhance growth velocity in pediatric patients with GHD.

12.2 Pharmacodynamics

Following single dose administration of somatrogon, dose-dependent increases in IGF-1 response were observed.

Following multiple dosing, IGF-1 SDS levels were in the normal range for pediatric patients with GHD, similar to daily somatropin. IGF-1 levels peak approximately 2 days (48 hours) post-dose, with the average weekly IGF-1 occurring approximately 4 days post-dose.

12.3 Pharmacokinetics

Somatrogon-ghla pharmacokinetics (PK) was assessed using a population PK approach for NGENLA in 151 pediatric patients (aged 3 to 15.5 years) with GHD.

Absorption

Following subcutaneous injection, serum concentrations increased slowly, peaking 6 to 25 hours with a median of 11 hours after dosing.

In pediatric patients with GHD, somatrogon-ghla exposure increases in a dose-proportional manner for doses of 0.25 mg/kg/wk, 0.48 mg/kg/wk, and 0.66 mg/kg/wk. There is no accumulation of somatrogon-ghla after once weekly administration. In pediatric patients with GHD, the mean population PK estimated steady-state peak concentrations (mean ± SD) following 0.66 mg/kg/wk was 495 ± 90 ng/mL.

Distribution

In pediatric patients with GHD, the mean population PK estimated apparent central volume of distribution was 0.342 L/kg and apparent peripheral volume of distribution was 0.671 L/kg.

Elimination

In pediatric patients with GHD, the mean population PK estimated apparent clearance was 0.0398 L/h/kg. The mean population PK estimated effective half-life was 37.7 hours, which allows for weekly dosing. Somatrogon-ghla will be present in the circulation for about 8 days after the last dose.

Metabolism

The metabolism of somatrogon-ghla is believed to be classical protein catabolism, with subsequent recovery of the amino acids and return to the systemic circulation.

Excretion

Excretion was not evaluated in clinical studies.

Specific Populations

Based on population PK analyses, age, sex, race, and ethnicity do not have a clinically meaningful effect on the pharmacokinetics of somatrogon-ghla in pediatric patients with GHD. The exposure of somatrogon-ghla decreases with an increase in body weight. However, the somatrogon-ghla dosing regimen of 0.66 mg/kg/wk provides adequate systemic exposure over the body weight range of 10 to 54 kg evaluated in the clinical studies.

Renal or Hepatic Impairment

NGENLA has not been studied in patients with hepatic or renal impairment.

12.6 Immunogenicity

The observed incidence of anti-drug antibodies is highly dependent on the sensitivity and specificity of the assay. Differences in assay methods preclude meaningful comparisons of the incidence of anti-drug antibodies in the studies described below with the incidence of anti-drug antibodies in other studies, including those of somatrogon or other growth hormone products.

During the 12-month main period of study NCT 02968004, 84/109 (77.1%) of somatrogon-ghla‑treated patients tested positive for anti-drug antibodies, with most showing specificity to human growth hormone. The anti-drug antibodies persisted in most of the subjects during the study. Neutralizing antibodies developed in 8/217 (3.7%) of somatrogon-ghla-treated patients during the study for up to 42 months of exposure to somatrogon-ghla. The neutralizing antibodies were transient in all subjects. Anti-drug antibodies, including neutralizing-antibodies, did not appear to have a clinically significant impact on the safety or effectiveness of NGENLA during the 12‑month randomized treatment period. Additionally, no apparent effect of anti-drug antibodies on growth was observed for additional 30 months of exposure to somatrogon-ghla in the uncontrolled extension period of study NCT 02968004.

Anti-Drug Antibody Effects on Pharmacokinetics

The population pharmacokinetic analysis of data from study NCT 02968004 showed that patients who tested positive for anti-drug antibodies had an approximately 26% decrease in apparent clearance. These anti-drug antibody-associated pharmacokinetic changes are not considered to be clinically significant.

13 NONCLINICAL TOXICOLOGY

13.1 Carcinogenesis, Mutagenesis, Impairment of Fertility

Carcinogenesis

No long term carcinogenicity studies have been performed with somatrogon-ghla.

Mutagenesis

Genotoxicity studies have not been performed.

Impairment of Fertility

The potential for somatrogon-ghla to affect fertility and early embryonic development was evaluated in male and female rats administered subcutaneously before cohabitation, through mating to implantation. Somatrogon‑ghla elicited an increase in estrous cycle length, copulatory interval, and number of corpora lutea at exposures ≥22-fold the MRHD, but there was no impact on female fertility, mating indices, number of viable embryos or early embryonic development, or on male fertility up to 30 mg/kg every two days (45-fold the MRHD based on exposure).

14 CLINICAL STUDIES

14.1 Treatment-Naïve Pediatric Patients with Growth Hormone Deficiency

A multi-center, randomized, open-label, active-controlled, parallel-group phase 3 study (NCT 02968004) was conducted in 224 treatment-naïve, prepubertal pediatric subjects with growth hormone deficiency (GHD). The primary efficacy endpoint was annualized height velocity at Week 52.

One hundred nine (109) subjects received 0.66 mg/kg/week NGENLA, and 115 subjects received 0.034 mg/kg/day daily somatropin. The subjects age ranged from 3 to 12 years, with a mean of 7.7 years. One hundred sixty-one (71.9%) subjects were male and 63 (28.1%) were female. One hundred sixty-seven (74.6%) subjects were White, 45 (20.1%) subjects were Asian, 2 (0.9%) subjects were Black or African-American, 1 (0.5%) subject was American Indian or Alaska Native, 1 (0.5%) subject was Native Hawaiian or Other Pacific Islander, and for 8 (3.6%) subjects race information was missing; 24 (10.7%) subjects identified as Hispanic or Latino. The subjects had a mean baseline height standard deviation score (SDS) of -2.9.

Treatment with once-weekly NGENLA for 52 weeks resulted in an annualized height velocity of 10.1 cm/year. Patients treated with daily somatropin achieved an annualized height velocity of 9.8 cm/year after 52 weeks of treatment. Refer to Table 3.

Table 3. Annualized Height Velocity at Week 52 in Pediatric Patients with GHD
Treatment Parameter | Treatment Group |  | LSM Treatment Difference (95% CI) (NGENLA minus Daily Somatropin)
Treatment Parameter | NGENLA (N=109) | Daily Somatropin (N=115) | LSM Treatment Difference (95% CI) (NGENLA minus Daily Somatropin)
 | LSM Estimate | LSM Estimate
Annualized Height Velocity (cm/yr) | 10.1 | 9.8 | 0.3 (-0.2, 0.9)
Abbreviations: CI=confidence interval; LSM=least square mean; N=number of patients randomized and treated
The estimates of LSM are from analysis of covariance model with treatment, age group, gender, peak growth hormone levels, and region as fixed factors and baseline height SDS as a covariate. Missing data is imputed by multiple imputation using SAS PROC MI with MNAR/FCS Method.

The mean height SDS at Week 52 was -1.94 in NGENLA arm and -1.99 in the daily somatropin arm. The mean increase in height SDS from baseline at Week 52 was 0.92 in NGENLA arm and 0.87 in the daily somatropin arm, respectively.

16 HOW SUPPLIED/STORAGE AND HANDLING

How Supplied

NGENLA (somatrogon-ghla) injection is a clear and colorless to slightly light yellow solution containing a preservative and supplied as one single-patient-use disposable prefilled pen per carton available in the following packages:

 | 24 mg/1.2 mL Prefilled Pen NDC: 0069-0505-02 | 60 mg/1.2 mL Prefilled Pen NDC: 0069-0520-02
Somatrogon-ghla solution concentration | 20 mg/mL | 50 mg/mL
Color scheme | Lilac pen cap, injection button and label | Blue pen cap, injection button and label
Dose increments | 0.2 mg/0.01 mL | 0.5 mg/0.01 mL
Maximum dose | 12 mg (0.6 mL) | 30 mg (0.6 mL)

Not made with natural rubber latex.

Sterile needles are required for administration but not included. Consult the Instructions for Use for needles that can be used.

Storage and Handling

Before first use: Store refrigerated at 36°F to 46°F (2°C to 8°C) in the original carton to protect from light.

After first use: Store the pen refrigerated at 36°F to 46°F (2°C to 8°C) between each use, for up to 28 days.

Do not freeze or shake. Do not expose to heat. Do not use if it has been frozen. Store away from direct sunlight.

Always remove and safely discard the needle after each injection and store the NGENLA prefilled pen without an injection needle attached. Always use a new needle for each injection. Replace the cap on your prefilled pen when it is not in use. Write the date of first use in the space provided on the pen label. The prefilled pen should not be used more than 28 days after first use.

17 PATIENT COUNSELING INFORMATION

Advise the patient and/or caregiver to read the FDA-approved patient labeling (Patient Information and Instructions for Use).

- Hypersensitivity Reactions
  Advise patients and caregivers that serious systemic hypersensitivity reactions (anaphylaxis and angioedema) are possible and that prompt medical attention should be sought if an allergic reaction occurs [see Warnings and Precautions (5.2)].
- Neoplasm
  Advise childhood cancer survivors and caregivers that individuals treated with radiation to the head are at increased risk of secondary neoplasms and, as a precaution, need to be monitored for recurrence. Advise patients to report marked changes in skin pigmentation or changes in the appearance of preexisting nevi [see Warnings and Precautions (5.3)].
- Glucose Intolerance/Diabetes Mellitus
  Advise patients and caregivers that new onset of insulin resistance and hyperglycemia may occur and monitoring of blood glucose during treatment with NGENLA in patients with glucose intolerance or who have risk factors for diabetes, may be needed [see Warnings and Precautions (5.4)].
- Intracranial Hypertension
  Advise patients and caregivers to report to their healthcare provider any visual changes, headache, and nausea and/or vomiting [see Warnings and Precautions (5.5)].
- Fluid Retention
  Advise patients and caregivers that fluid retention during NGENLA therapy may occur. Inform patients of the clinical manifestations of fluid retention (e.g. edema, arthralgia, myalgia, nerve compression syndromes including carpal tunnel syndrome/paresthesia) and to report to their healthcare provider if any of these signs or symptoms occur during treatment with NGENLA.
- Hypoadrenalism
  Advise patients and caregivers who have or who are at risk for corticotropin deficiency that hypoadrenalism may develop and to report to their healthcare provider if extreme fatigue, dizziness, weakness, vomiting, dehydration or weight loss is experienced during treatment with NGENLA [see Warnings and Precautions (5.7)].
- Hypothyroidism
  Advise patients and caregivers that undiagnosed/untreated hypothyroidism may prevent an optimal response to NGENLA. Advise patients and caregivers they may require periodic thyroid function tests during treatment with NGENLA [see Warnings and Precautions (5.8)].
- Pancreatitis
  Advise patients and caregivers that pancreatitis may develop and to report to their healthcare provider any new onset persistent severe abdominal pain.
- Lipoatrophy
  Advise patients and caregivers that lipoatrophy may occur if NGENLA is administered subcutaneously at the same site over a long period of time. Advise patients to rotate injection sites when administering NGENLA to reduce this risk.

Manufactured by:
Pfizer Ireland Pharmaceuticals
Ringaskiddy,
Cork,
Ireland

US License No: 2060

This product’s labeling may have been updated. For the most recent prescribing information, please visit www.pfizer.com.

LAB-1433-2.0

PATIENT INFORMATION
NGENLA® (en’ JEN-lah)

(somatrogon-ghla)

injection, for subcutaneous use

What is NGENLA?
NGENLA is a prescription medicine that contains a form of human growth hormone, like the growth hormone made by the human body. NGENLA is given by injection under the skin (subcutaneous) in children who are not growing because of low or no growth hormone levels.

Do not use NGENLA if:

- your child has a critical illness caused by certain types of heart or stomach surgery, trauma or breathing (respiratory) problems.
- your child is allergic to somatrogon-ghla or any of the ingredients in NGENLA. See the end of this leaflet for a complete list of ingredients in NGENLA.
- your child has closed bone growth plates (epiphyses).
- your child has cancer or other tumors.
- your child’s healthcare provider tells you that your child has certain types of eye problems caused by diabetes (diabetic retinopathy).
- your child has Prader-Willi syndrome, is severely obese, or has breathing problems including sleep apnea (briefly stop breathing during sleep).

Before using NGENLA, tell your child’s healthcare provider about all of your child’s medical conditions, including if your child:

- has had heart or stomach surgery, trauma or serious breathing (respiratory) problems.
- has had a history of problems breathing while they slept (sleep apnea).
- has or has had cancer or any tumor.
- has diabetes.
- is pregnant or plans to become pregnant. It is not known if NGENLA will harm your child’s unborn baby. Talk to your child’s healthcare provider if your child is pregnant or plans to become pregnant.
- is breastfeeding or plans to breastfeed. It is not known if NGENLA passes into breast milk. You and your child’s healthcare provider should decide if they will take NGENLA while breastfeeding.

Tell your child’s healthcare provider about all the medicines your child takes, including prescription and over-the-counter medicines, vitamins, and herbal supplements. NGENLA may affect how other medicines work, and other medicines may affect how NGENLA works.

How should I use NGENLA?

- Read the detailed Instructions for Use that come with NGENLA.
- NGENLA comes in 2 different dosage strengths. Your child’s healthcare provider will prescribe the dose of medicine and the dosage strength that is right for your child.
- Your child’s healthcare provider will show you how to inject NGENLA before it is used for the first time. Do not try to inject NGENLA until you have been shown the right way by your child’s healthcare provider.
- Inject NGENLA exactly as your child’s healthcare provider tells you to.
- NGENLA is injected under the skin (subcutaneously) and can be given in the stomach (abdomen), thighs, buttocks, or upper arms. Rotate the site of injection weekly.
- Inject NGENLA 1 time each week, on the same day each week, at any time of the day.
- You may change the day of the week NGENLA is used as long as the last dose was injected 3 or more days before. After the new day of the week has been chosen, continue with the 1 time a week schedule.
- If your child misses a dose of NGENLA the missed dose should be injected as soon as possible within 3 days after the missed dose. If more than 3 days have passed, skip your child’s missed dose. Inject the next dose on the regularly scheduled day.
- NGENLA prefilled pens are for use by 1 person only.
- Do not share your child’s NGENLA prefilled pens and needles with another person, even if the needle has been changed. Your child may give another person an infection or get an infection from them.

What are the possible side effects of NGENLA?

NGENLA may cause serious side effects, including:

- high risk of death in people who have critical illnesses because of heart or stomach surgery, trauma or serious breathing (respiratory) problems.
- serious allergic reactions. Get medical help right away if your child has the following symptoms:
  - swelling of the face, lips, mouth, or tongue
  - trouble breathing
  - wheezing
  - severe itching
  - skin rashes, redness, or swelling
  - dizziness or fainting
  - fast heartbeat or pounding in the chest
  - sweating
- increased risk of growth of cancer or a tumor that is already present and increased risk of the return of cancer or a tumor in people who were treated with radiation to the brain or head as children and who developed low growth hormone problems. Your child’s healthcare provider will need to monitor your child for a return of cancer or a tumor. Contact your child’s healthcare provider if your child starts to have headaches, or has changes in behavior, changes in vision, or changes in moles, birthmarks, or the color of the skin.
- new or worsening high blood sugar (hyperglycemia) or diabetes. Your child’s blood sugar may need to be monitored during treatment with NGENLA.
- increase in pressure inside the skull (intracranial hypertension). If your child has headaches, eye problems, nausea or vomiting, contact your child’s healthcare provider.
- your child’s body holding too much fluid (fluid retention) such as swelling in the hands and feet, pain in the joints or muscles or nerve problems that cause pain, burning or tingling in the hands, arms, legs and feet. Fluid retention can happen in children during treatment with NGENLA. Tell your child’s healthcare provider if your child has any of these signs or symptoms of fluid retention.
- decrease in a hormone called cortisol. Your child’s healthcare provider will do blood tests to check your child’s cortisol levels. Tell your child’s healthcare provider if your child has severe fatigue, dizziness, weakness, vomiting, dehydration, or weight loss.
- decrease in thyroid hormone levels. Decreased thyroid hormone levels may affect how well NGENLA works. Your child’s healthcare provider will do blood tests to check your child’s hormone levels.
- hip and knee pain or limp (slipped capital femoral epiphysis). This may lead to a serious condition where bone tissue dies due to a lack of blood supply (osteonecrosis). Get medical help for your child right away if your child develops a limp or has hip or knee pain.
- worsening of curvature of the spine (scoliosis). If your child has scoliosis, your child will need to be checked often for an increase in the curve of the spine.
- severe and constant stomach (abdominal) pain. This could be a sign of pancreatitis. Tell your child’s healthcare provider if your child has any new abdominal pain.
- loss of fat and tissue weakness in the area of skin you inject. Talk to your child’s healthcare provider about rotating the areas where you inject NGENLA.
- high risk of sudden death in children with Prader-Willi syndrome who are severely obese or have breathing problems, including sleep apnea.
- increase in phosphorus, alkaline phosphatase and parathyroid hormone levels in the blood. Your child’s healthcare provider will do blood tests to check this.

The most common side effects of NGENLA include:

  - injection site reactions (such as pain, swelling, rash, itching, bleeding)
  - common cold
  - headache
  - fever
  - low red blood cells (anemia)
  - cough
  - vomiting
  - decrease in thyroid hormone levels
  - stomach (abdominal) pain
  - rash
  - throat pain

These are not all the possible side effects of NGENLA. You should tell your child’s healthcare provider if your child has any side effect that bothers them or that does not go away.
Call your child’s doctor for medical advice about side effects. You may report side effects to FDA at 1-800-FDA-1088.

How should I store NGENLA?

- Do not freeze your pen or expose it to heat.
- Do not use your pen if it has been frozen or stored in direct sunlight.
- Do not use after the expiration date printed on the label has passed or if it has been more than 28 days after first use.

Before you use NGENLA pens for the first time (unused pens):

- Store in the original carton.
- Store the new, unused NGENLA pen in the refrigerator between 36°F to 46°F (2°C to 8°C).
- Unused prefilled pens may be used until the expiration date printed on the pen label, if kept in the refrigerator.

After you use NGENLA pens and there is still medicine left (up to 28 days of use):

- To help you remember when to dispose of (throw away) the pen, write the date of first use on the pen label.
- Store remaining NGENLA in the refrigerator between 36°F to 46°F (2°C to 8°C) and use within 28 days.
- Keep the pen cap on the NGENLA pen when it is not in use.
- Do not store the remaining NGENLA pen with a needle attached.
- Do not use the NGENLA pen if it has been more than 28 days after first use, even if it contains unused medicine.

Keep NGENLA and all medicines out of the reach of children.

General information about the safe and effective use of NGENLA.

Medicines are sometimes prescribed for purposes other than those listed in a Patient Information leaflet. Do not use NGENLA for a condition for which it was not prescribed. Do not give NGENLA to other people, even if they have the same symptoms because it may harm them. You can ask your pharmacist or healthcare provider for information about NGENLA that is written for health professionals.

What are the ingredients in NGENLA?

Active ingredient: somatrogon-ghla

Inactive ingredients: citric acid monohydrate, histidine, metacresol (as a preservative), poloxamer 188, sodium chloride, sodium citrate, water for injection.
This product's labeling may have been updated. For the most recent prescribing information, please visit www.pfizer.com.

Manufactured by:
Pfizer Ireland Pharmaceuticals
Ringaskiddy,
Cork,
Ireland
US License No: 2060

LAB-1449-2.0
For more information, go to website www.NGENLA.com or call 1-800-438-1985.

This Patient Information has been approved by the U.S. Food and Drug Administration. Revised: 07/2025

Instructions for Use

NGENLA® (en’ JEN-lah)

(somatrogon-ghla)

24 mg
injection, for subcutaneous use

Read this Instructions for Use before you start using NGENLA and each time you get a new refill. There may be new information. This information does not take the place of talking to your healthcare provider about your medical condition or treatment.

Important information about your NGENLA pen:

- The NGENLA pen for injection is a single-patient-use, disposable (throw away) prefilled pen containing 24 mg of medicine. You can give more than 1 dose from the pen.
- NGENLA can be given by a patient, caregiver or healthcare provider. Do not try to inject NGENLA yourself until you are shown the right way to give the injections and read and understand the Instructions for Use. If your healthcare provider decides that you or a caregiver may be able to give your injections of NGENLA at home, you should receive training on the right way to prepare and inject NGENLA. It is important that you read, understand, and follow these instructions so that you inject NGENLA the right way.
- It is important to talk to your healthcare provider to be sure you understand your NGENLA dosing instructions. To help you remember when to inject NGENLA, you can mark your calendar ahead of time. Call your healthcare provider if you or your caregiver have any questions about the right way to inject NGENLA, or call the helpline on 1-800-645-1280.
- Do not share your pen with other people, even if the needle has been changed. You may give other people a serious infection or get a serious infection from them.
- Each turn (click) of the dose knob dials 0.2 mg of medicine. You can give from 0.2 mg to 12 mg in a single injection. If your dose is more than 12 mg, you will need to give more than 1 injection.
- A new pen may contain slightly more than 24 mg of medicine, this is normal.
- Always use a new sterile needle for each injection. This will decrease the risk of contamination, infection, leakage of medicine, and blocked needles leading to the wrong dose.
- Do not shake your pen. Shaking can damage the medicine.
- The pen is not recommended for use by the blind or visually impaired without the assistance of a person trained in the proper use of the product.

Supplies you will need each time you inject

Included in the carton:

- 1 NGENLA prefilled pen

Not included in the carton:

- 1 new sterile needle for each injection
- Alcohol swabs
- Cotton balls or gauze pads
- Adhesive bandage
- 1 FDA-cleared sharps disposal container for disposal of pen needles and pens (See How should I dispose of the pen needles and pens?)

24 mg NGENLA pen:

Needles to use

Pen needles are not included with your NGENLA pen. You will need a prescription from your healthcare provider to get pen needles up to a length of 8 mm from your pharmacy. Talk with your healthcare provider about the right needle for you.

- Needles to use with your NGENLA pen:
  - 32G (Novo Nordisk®, NovoFine® Plus)
  - 31G (Novo Nordisk®, NovoFine®)
  - 31G (Becton, Dickinson and Company, BD Ultra-Fine™ or BD Micro-Fine™)
- Needles with safety shield to use with your NGENLA pen:
  - 30G (Becton, Dickinson and Company, AutoShield Duo™)
  - 30G (Novo Nordisk®, NovoFine® AutoCover®)

Sterile needle (example) not supplied:

Sterile needle with safety shield (example) not supplied:

Note: Needles with safety shield do not have an inner needle cap. Steps 5, 6 and 11 within these instructions relating to the inner needle cap may not apply when using a needle with safety shield. Refer to the safety shield needle manufacturer’s instructions for use (IFU) for more information on attaching and removing the safety needle. When using safety shield needles, priming is required only for the first use of a new pen; follow the NGENLA pen IFU for priming.

Caution: Never use a bent or damaged needle. Always handle pen needles with care to make sure you do not prick yourself (or anyone else) with the needle. Do not attach a new needle to your pen until you are ready to take your injection.

Preparing for your injection

Step 1 - Getting ready

- Wash and dry your hands.
- You can use your pen straight from the refrigerator. For a more comfortable injection, leave your pen at room temperature for up to 30 minutes.
- Check the name, strength, and label of your pen to make sure it is the medicine your healthcare provider has prescribed for you.
- Check the expiration date on the pen label. Do not use if the expiration date has passed.
- Do not use your pen if:
  - it has been frozen or exposed to heat
  - it has been dropped
  - it looks broken or damaged
  - it has been more than 28 days after first use of the pen.
- Do not remove the pen cap from your pen - until you are ready to inject.

Step 2 - Choose and clean your injection site

- NGENLA can be given in the abdomen, thighs, buttocks, or upper arms.
- Choose the best place to inject, as recommended by your healthcare provider.
- If more than 1 injection is needed to complete your full dose, each injection should be given in a different injection site.
- Do not inject into bony areas, areas that are bruised, red, sore or hard, and areas that have scars or skin conditions.
- Clean the injection site with an alcohol swab.
- Allow the injection site to dry.
- Do not touch injection site after cleaning.

Step 3 - Check medicine

- Pull off the pen cap and keep it for after your injection.
- Check the medicine inside the cartridge holder.
- Make sure the medicine is colorless to slightly light yellow. Do not inject the medicine if it is cloudy or dark yellow.
- Make sure the medicine is free of flakes or particles. Do not inject the medicine if it has flakes or particles.
  Note: It is normal to see one or more bubbles in the medicine.

Step 4 - Attach needle

- Take a new needle and pull off the protective paper.
- Line the needle up with your pen keeping them both straight.
- Gently push and then screw the needle onto your pen.
  Do not over tighten.
  Note: Be careful not to attach the needle at an angle. This may cause the pen to leak.
  Caution: Needles have sharp tips at both ends. Handle with care to make sure you do not prick yourself (or anyone else) with the needle.

Step 5 - Pull off outer needle cover

- Pull off the outer needle cover.
- Make sure you keep the outer needle cover. You will need it later to remove the needle.
  Note: You should see an inner needle cap after you have removed the outer cover. If you do not see this, try to attach the needle again.
  Note: Needles with safety shield do not have an inner needle cap. Refer to the safety shield needle manufacturer’s IFU.

Step 6 - Pull off inner needle cap

- Pull off the inner needle cap carefully to show the needle.
- Throw away the inner needle cap in an FDA-cleared sharps container. It is not needed again.
  Note: Needles with safety shield do not have an inner needle cap. Refer to the safety shield needle manufacturer’s IFU.

Is this pen new?

Yes: Go to new pen set up (arrow directing to “New pen set up (priming) - for the first use of a new pen only”)

No (arrow directing to “Setting your prescribed dose”)

New pen set up (priming) – for the first use of a new pen only

You must set up each new pen (priming) before using it for the first time

- New pen set up is done before each new pen is used for the first time.
- The purpose of setting up a new pen is to remove air bubbles and make sure you get the correct dose.
  Important: Skip Step-A through to Step-C if you have already set up your pen.
  Note: Needles with safety shield should be primed once with first use of a new pen.

A - Set priming dose

- Turn the dose knob to 0.4.
  - This is the amount to prime the pen.
Note: If you turn the dose knob too far, you can turn it back.

B - Tap cartridge holder

- Hold the pen with the needle pointing up so that the air bubbles can rise.
- Tap the cartridge holder gently to float any air bubbles to the top.
  Important: Follow Step-B even if you do not see air bubbles.

C - Press button and check for liquid

- Press the injection button until it cannot go any further and "0" is shown in the dose window.
- Check for liquid at the needle tip. If liquid appears, your pen is set up.
- Always make sure that a drop of liquid appears before you inject. If liquid has not appeared, repeat Step-A through to Step-C.
  - If liquid does not appear after you have repeated Step-A through Step-C five (5) times, attach a new needle and try 1 more time. Do not use the pen if a drop of liquid still does not appear. Contact your healthcare provider or pharmacist and use a new pen.

Setting your prescribed dose

Step 7 - Set your dose

Example A:

3.8 mg shown in the dose window

Example B:

12.0 mg shown in the dose window

- Turn the dose knob to set your dose.
  - The dose can be increased or decreased by turning the dose knob in either direction.
  - The dose knob turns 0.2 mg at a time.
  - Your pen contains 24 mg of medicine but you can only set a dose of up to 12 mg for a single injection.
  - The dose window shows the dose in mg. See Examples A and B.
- Always check the dose window to make sure you have set the correct dose.
  Important: Do not press the injection button while setting your dose.

What should I do if I cannot set the dose I need?

- If your dose is more than 12 mg you will need to split your dose into more than 1 injection.
- You can give from 0.2 mg to 12 mg in a single injection.
  - Use a new needle for each injection (See Step 4: Attach needle).
  - If you normally need to give 2 injections for your full dose, be sure to give your second dose.

What should I do if I do not have enough medicine left in my pen?

- If your pen contains less than 12 mg of medicine, the dose knob will stop with the remaining amount of medicine shown in the dose window.
- If there is not enough medicine left in your pen for your full dose, you may either:
  - Inject the amount left in your pen, then prepare a new pen to complete your dose in full. Remember to subtract the dose you have already received. For example, if the dose is 3.8 mg and you can only set the dose knob to 1.8 mg, you should inject another 2.0 mg with a new pen.
  - Or get a new pen and inject the full dose.

Only split your dose if you have been trained or told by your healthcare provider on how to do this.

Injecting your dose

Step 8 - Insert the needle

- Hold your pen so you can see the numbers in the dose window.
- Insert the needle straight into your skin.
  Note: If using needles with safety shield, you may wish to stretch or pinch the skin at the injection site to make the injection easier.

Step 9 - Inject your medicine

- Keep holding the needle in the same position in your skin.
- Press the injection button until it cannot go any further and "0" is shown in the dose window.

Step 10 - Count to 10

- Continue to press the injection button while counting to 10. Counting to 10 will allow the full dose of medicine to be given.
- After counting to 10, let go of the injection button and slowly remove the pen from the injection site by pulling the needle straight out.
  Note: You may see a drop of medicine at the needle tip. This is normal and does not affect the dose you just received.

Step 11 - Attach outer needle cover

- Carefully place the outer needle cover back on the needle.
- Press on the outer needle cover until it is secure.
  Caution: Never try to put the inner needle cap back on the needle. You may prick yourself with the needle.
  Note: If using needle with safety shield, refer to the safety shield needle manufacturer’s IFU.

Step 12 - Remove the needle

- Unscrew the needle from the pen.
- Gently pull until the needle comes off.
  Note: If the needle is still on, replace the outer needle cover and try again. Be sure to apply pressure when unscrewing the needle.
- Throw away the needle in an FDA-cleared sharps container (See How should I dispose of the pen needles and pens?).
- Important: Always remove and throw away used needles. Do not reuse needles.

Step 13 - Replace the pen cap

- Replace the pen cap back onto your pen.
- Do not recap the pen with a needle attached.
- If there is any medicine left in your pen, store in the refrigerator between uses (See How should I store my pen?).

Step 14 - After your injection

- Press lightly on the injection site with a clean cotton ball or gauze pad, and hold for a few seconds.
- Do not rub the injection site. You may have slight bleeding. This is normal.
- You may cover the injection site with a small adhesive bandage, if needed.
- If your pen is empty or it has been more than 28 days after first use, throw it away even if it contains unused medicine. See Storage and disposal on the right side of this leaflet.

Storage and disposal:

How should I store my pen?

- Do not freeze your pen or expose it to heat.
- Do not use your pen if it has been frozen or stored in direct sunlight.
- Do not use after the expiration date printed on the label has passed or if it has been more than 28 days after first use.
- Keep NGENLA and all medicines out of the reach of children.

Before first use (unused pens):

- Store in the original carton.
- Store your pens in the refrigerator between 36°F to 46°F (2°C to 8°C).
- Unused pens may be used until the expiration date printed on the label, only if the pen has been kept in the refrigerator.

After first use (up to 28 days of use):

- Store your pen in the refrigerator between 36°F to 46°F (2°C to 8°C) and away from direct sunlight.
- Keep the pen cap on your pen when it is not in use.
- Do not store the pen with a needle attached.
- If your pen is empty or it has been more than 28 days after first use, throw it away even if it contains unused medicine.
- To help you remember when to dispose of your pen you can write the date of first use on the pen label and below:
  Date of first use ______ / ______ / ______

How should I dispose of the pen needles and pens?

- Throw away your pen, and pen needles into an FDA-cleared sharps disposal container or puncture resistant container.
- If you do not have an FDA-cleared sharps disposal container, you may use a household container that:
  - is made of heavy-duty plastic
  - can be closed with a tight-fitting, puncture resistant lid, without sharps being able to come out
  - is upright and stable during use
  - is leak-resistant, and properly labeled to warn of hazardous waste inside the container.
- When your sharps disposal container is almost full, you will need to follow your community guidelines for the right way to dispose of your sharps disposal container. There may be state or local laws about how you should throw away used needles, syringes, and prefilled syringes.
- For more information about safe sharps disposal, and for specific information about sharps disposal in the state that you live in, go to the FDA's website at: https://www.fda.gov/safesharpsdisposal
- Do not throw away your used sharps disposal container in your household trash unless your community guidelines permit this.
- Keep the sharps container out of the reach of children.

Manufactured by:
Pfizer Ireland Pharmaceuticals
Ringaskiddy,
Cork,
Ireland

US License No: 2060
LAB-1452-2.0

This Instructions for Use has been approved by the U.S. Food and Drug Administration. Revised: 7/2024

Instructions for Use
NGENLA® (en’ JEN-lah)

(somatrogon-ghla)
60 mg
injection, for subcutaneous use

Read this Instructions for Use before you start using NGENLA and each time you get a new refill. There may be new information. This information does not take the place of talking to your healthcare provider about your medical condition or treatment.

Important information about your NGENLA pen:

- The NGENLA pen for injection is a single-patient-use, disposable (throw away) prefilled pen containing 60 mg of medicine. You can give more than 1 dose from the pen.
- NGENLA can be given by a patient, caregiver or healthcare provider. Do not try to inject NGENLA yourself until you are shown the right way to give the injections and read and understand the Instructions for Use. If your healthcare provider decides that you or a caregiver may be able to give your injections of NGENLA at home, you should receive training on the right way to prepare and inject NGENLA. It is important that you read, understand, and follow these instructions so that you inject NGENLA the right way.
- It is important to talk to your healthcare provider to be sure you understand your NGENLA dosing instructions. To help you remember when to inject NGENLA, you can mark your calendar ahead of time. Call your healthcare provider if you or your caregiver have any questions about the right way to inject NGENLA, or call the helpline on 1-800-645-1280.
- Do not share your pen with other people, even if the needle has been changed. You may give other people a serious infection or get a serious infection from them.
- Each turn (click) of the dose knob dials 0.5 mg of medicine. You can give from 0.5 mg to 30 mg in a single injection. If your dose is more than 30 mg, you will need to give more than 1 injection.
- A new pen may contain slightly more than 60 mg of medicine, this is normal.
- Always use a new sterile needle for each injection. This will decrease the risk of contamination, infection, leakage of medicine, and blocked needles leading to the wrong dose.
- Do not shake your pen. Shaking can damage the medicine.
- The pen is not recommended for use by the blind or visually impaired without the assistance of a person trained in the proper use of the product.

Supplies you will need each time you inject

Included in the carton:

- 1 NGENLA prefilled pen

Not included in the carton:

- 1 new sterile needle for each injection
- Alcohol swabs
- Cotton balls or gauze pads
- Adhesive bandage
- 1 FDA-cleared sharps disposal container for disposal of pen needles and pens (See How should I dispose of the pen needles and pens?)

60 mg NGENLA pen:

Needles to use

Pen needles are not included with your NGENLA pen. You will need a prescription from your healthcare provider to get pen needles up to a length of 8 mm from your pharmacy. Talk with your healthcare provider about the right needle for you.

- Needles to use with your NGENLA pen:
  - 32G (Novo Nordisk®, NovoFine® Plus)
  - 31G (Novo Nordisk®, NovoFine®)
  - 31G (Becton, Dickinson and Company, BD Ultra-Fine™ or BD Micro-Fine™)
- Needles with safety shield to use with your NGENLA pen:
  - 30G (Becton, Dickinson and Company, AutoShield Duo™)
  - 30G (Novo Nordisk®, NovoFine® AutoCover®)

Sterile needle (example) not supplied:

Sterile needle with safety shield (example) not supplied:

Note: Needles with safety shield do not have an inner needle cap. Steps 5, 6 and 11 within these instructions relating to the inner needle cap may not apply when using a needle with safety shield. Refer to the safety shield needle manufacturer’s instructions for use (IFU) for more information on attaching and removing the safety needle. When using safety shield needles, priming is required only for the first use of a new pen; follow the NGENLA pen IFU for priming.

Caution: Never use a bent or damaged needle. Always handle pen needles with care to make sure you do not prick yourself (or anyone else) with the needle. Do not attach a new needle to your pen until you are ready to take your injection.

Preparing for your injection

Step 1 - Getting ready

- Wash and dry your hands.
- You can use your pen straight from the refrigerator. For a more comfortable injection, leave your pen at room temperature for up to 30 minutes.
- Check the name, strength, and label of your pen to make sure it is the medicine your healthcare provider has prescribed for you.
- Check the expiration date on the pen label. Do not use if the expiration date has passed.
- Do not use your pen if:
  - it has been frozen or exposed to heat
  - it has been dropped
  - it looks broken or damaged
  - it has been more than 28 days after first use of the pen.
- Do not remove the pen cap from your pen - until you are ready to inject.

Step 2 - Choose and clean your injection site

- NGENLA can be given in the abdomen, thighs, buttocks, or upper arms.
- Choose the best place to inject, as recommended by your healthcare provider.
- If more than 1 injection is needed to complete your full dose, each injection should be given in a different injection site.
- Do not inject into bony areas, areas that are bruised, red, sore or hard, and areas that have scars or skin conditions.
- Clean the injection site with an alcohol swab.
- Allow the injection site to dry.
- Do not touch injection site after cleaning.

Step 3 - Check medicine

- Pull off the pen cap and keep it for after your injection.
- Check the medicine inside the cartridge holder.
- Make sure the medicine is colorless to slightly light yellow. Do not inject the medicine if it is cloudy or dark yellow.
- Make sure the medicine is free of flakes or particles. Do not inject the medicine if it has flakes or particles.
  Note: It is normal to see one or more bubbles in the medicine.

Step 4 - Attach needle

- Take a new needle and pull off the protective paper.
- Line the needle up with your pen keeping them both straight.
- Gently push and then screw the needle onto your pen.
  Do not over tighten.
  Note: Be careful not to attach the needle at an angle. This may cause the pen to leak.
  Caution: Needles have sharp tips at both ends. Handle with care to make sure you do not prick yourself (or anyone else) with the needle.

Step 5 - Pull off outer needle cover

- Pull off the outer needle cover.
- Make sure you keep the outer needle cover. You will need it later to remove the needle.
  Note: You should see an inner needle cap after you have removed the outer cover. If you do not see this, try to attach the needle again.
  Note: Needles with safety shield do not have an inner needle cap. Refer to the safety shield needle manufacturer’s IFU.

Step 6 - Pull off inner needle cap

- Pull off the inner needle cap carefully to show the needle.
- Throw away the inner needle cap in an FDA-cleared sharps container. It is not needed again.
  Note: Needles with safety shield do not have an inner needle cap. Refer to the safety shield needle manufacturer’s IFU.

Is this pen new?

Yes: Go to new pen set up (arrow directing to “New pen set up (priming) - for the first use of a new pen only”)

No (arrow directing to “Setting your prescribed dose”)

New pen set up (priming) – for the first use of a new pen only

You must set up each new pen (priming) before using it for the first time

- New pen set up is done before each new pen is used for the first time.
- The purpose of setting up a new pen is to remove air bubbles and make sure you get the correct dose.
  Important: Skip Step-A through to Step-C if you have already set up your pen.
  Note: Needles with safety shield should be primed once with first use of a new pen.

A - Set priming dose

- Turn the dose knob to 1.0.
  - This is the amount to prime the pen.
Note: If you turn the dose knob too far, you can turn it back.

B - Tap cartridge holder

- Hold the pen with the needle pointing up so that the air bubbles can rise.
- Tap the cartridge holder gently to float any air bubbles to the top.
  Important: Follow Step-B even if you do not see air bubbles.

C - Press button and check for liquid

- Press the injection button until it cannot go any further and "0" is shown in the dose window.
- Check for liquid at the needle tip. If liquid appears, your pen is set up.
- Always make sure that a drop of liquid appears before you inject. If liquid has not appeared, repeat Step-A through to Step-C.
  - If liquid does not appear after you have repeated Step-A through Step-C five (5) times, attach a new needle and try 1 more time. Do not use the pen if a drop of liquid still does not appear. Contact your healthcare provider or pharmacist and use a new pen.

Setting your prescribed dose

Step 7 - Set your dose

Example A:

21.5 mg shown in the dose window

Example B:

30.0 mg shown in the dose window

- Turn the dose knob to set your dose.
  - The dose can be increased or decreased by turning the dose knob in either direction.
  - The dose knob turns 0.5 mg at a time.
  - Your pen contains 60 mg of medicine but you can only set a dose of up to 30 mg for a single injection.
  - The dose window shows the dose in mg. See Examples A and B.
- Always check the dose window to make sure you have set the correct dose.
  Important: Do not press the injection button while setting your dose.

What should I do if I cannot set the dose I need?

- If your dose is more than 30 mg you will need to split your dose into more than 1 injection.
- You can give from 0.5 mg to 30 mg in a single injection.
  - Use a new needle for each injection (See Step 4: Attach needle).
  - If you normally need to give 2 injections for your full dose, be sure to give your second dose.

What should I do if I do not have enough medicine left in my pen?

- If your pen contains less than 30 mg of medicine, the dose knob will stop with the remaining amount of medicine shown in the dose window.
- If there is not enough medicine left in your pen for your full dose, you may either:
  - Inject the amount left in your pen, then prepare a new pen to complete your dose in full. Remember to subtract the dose you have already received. For example, if the dose is 21.5 mg and you can only set the dose knob to 17 mg, you should inject another 4.5 mg with a new pen.
  - Or get a new pen and inject the full dose.

Only split your dose if you have been trained or told by your healthcare provider on how to do this.

Injecting your dose

Step 8 - Insert the needle

- Hold your pen so you can see the numbers in the dose window.
- Insert the needle straight into your skin.
  Note: If using needles with safety shield, you may wish to stretch or pinch the skin at the injection site to make the injection easier.

Step 9 - Inject your medicine

- Keep holding the needle in the same position in your skin.
- Press the injection button until it cannot go any further and "0" is shown in the dose window.

Step 10 - Count to 10

- Continue to press the injection button while counting to 10. Counting to 10 will allow the full dose of medicine to be given.
- After counting to 10, let go of the injection button and slowly remove the pen from the injection site by pulling the needle straight out.
  Note: You may see a drop of medicine at the needle tip. This is normal and does not affect the dose you just received.

Step 11 - Attach outer needle cover

- Carefully place the outer needle cover back on the needle.
- Press on the outer needle cover until it is secure.
  Caution: Never try to put the inner needle cap back on the needle. You may prick yourself with the needle.
  Note: If using needle with safety shield, refer to the safety shield needle manufacturer’s IFU.

Step 12 - Remove the needle

- Unscrew the needle from the pen.
- Gently pull until the needle comes off.
  Note: If the needle is still on, replace the outer needle cover and try again. Be sure to apply pressure when unscrewing the needle.
- Throw away the needle in an FDA-cleared sharps container (See How should I dispose of the pen needles and pens?).
- Important: Always remove and throw away used needles. Do not reuse needles.

Step 13 - Replace the pen cap

- Replace the pen cap back onto your pen.
- Do not recap the pen with a needle attached.
- If there is any medicine left in your pen, store in the refrigerator between uses (See How should I store my pen?).

Step 14 - After your injection

- Press lightly on the injection site with a clean cotton ball or gauze pad, and hold for a few seconds.
- Do not rub the injection site. You may have slight bleeding. This is normal.
- You may cover the injection site with a small adhesive bandage, if needed.
- If your pen is empty or it has been more than 28 days after first use, throw it away even if it contains unused medicine. See Storage and disposal on the right side of this leaflet.

Storage and disposal:

How should I store my pen?

- Do not freeze your pen or expose it to heat.
- Do not use your pen if it has been frozen or stored in direct sunlight.
- Do not use after the expiration date printed on the label has passed or if it has been more than 28 days after first use.
- Keep NGENLA and all medicines out of the reach of children.

Before first use (unused pens):

- Store in the original carton.
- Store your pens in the refrigerator between 36°F to 46°F (2°C to 8°C).
- Unused pens may be used until the expiration date printed on the label, only if the pen has been kept in the refrigerator.

After first use (up to 28 days of use):

- Store your pen in the refrigerator between 36°F to 46°F (2°C to 8°C) and away from direct sunlight.
- Keep the pen cap on your pen when it is not in use.
- Do not store the pen with a needle attached.
- If your pen is empty or it has been more than 28 days after first use, throw it away even if it contains unused medicine.
- To help you remember when to dispose of your pen you can write the date of first use on the pen label and below:
  Date of first use ______ / ______ / ______

How should I dispose of the pen needles and pens?

- Throw away your pen, and pen needles into an FDA-cleared sharps disposal container or puncture resistant container.
- If you do not have an FDA-cleared sharps disposal container, you may use a household container that:
  - is made of heavy-duty plastic
  - can be closed with a tight-fitting, puncture resistant lid, without sharps being able to come out
  - is upright and stable during use
  - is leak-resistant, and properly labeled to warn of hazardous waste inside the container.
- When your sharps disposal container is almost full, you will need to follow your community guidelines for the right way to dispose of your sharps disposal container. There may be state or local laws about how you should throw away used needles, syringes, and prefilled syringes.
- For more information about safe sharps disposal, and for specific information about sharps disposal in the state that you live in, go to the FDA’s website at: https://www.fda.gov/safesharpsdisposal
- Do not throw away your used sharps disposal container in your household trash unless your community guidelines permit this.
- Keep the sharps container out of the reach of children.

Manufactured by:
Pfizer Ireland Pharmaceuticals
Ringaskiddy,
Cork,
Ireland

US License No: 2060
LAB-1454-2.0

This Instructions for Use has been approved by the U.S. Food and Drug Administration. Revised: 7/2024

PRINCIPAL DISPLAY PANEL - 24 mg Cartridge Label

NDC 0069-0505-01
Store refrigerated

24mg

Ngenla®
(somatrogon-ghla)
Injection
24 mg/1.2 mL (20 mg/mL)
For Subcutaneous Injection Only

mg

Single-patient-use
Rx only

PRINCIPAL DISPLAY PANEL - 24 mg Cartridge Carton

One single-patient-use
disposable prefilled pen
Rx only
NDC 0069-0505-02

24mg

Ngenla®
(somatrogon-ghla)
Injection
24 mg/1.2 mL (20 mg/mL)
For Subcutaneous Injection Only

READ ENCLOSED INSTRUCTIONS BEFORE USE

Write the date of first use in the space provided on the
pen label. Discard the pen 28 days after first use, even if it
contains unused medicine.

Before first use: Store refrigerated at 36°F to 46°F (2°C to 8°C)
in the original carton to protect from light. After first use: Store
refrigerated at 36°F to 46°F (2°C to 8°C) between each use for up
to 28 days. Do not freeze or shake. Do not expose to heat.
Store away from direct sunlight. Do not use if it has been frozen.

PRINCIPAL DISPLAY PANEL - 60 mg Cartridge Label

NDC 0069-0520-01
Store refrigerated

60mg

Ngenla®
(somatrogon-ghla)
Injection
60 mg/1.2 mL (50 mg/mL)
For Subcutaneous Injection Only

mg

Single-patient-use
Rx only

PRINCIPAL DISPLAY PANEL - 60 mg Cartridge Carton

One single-patient-use
disposable prefilled pen
Rx only
NDC 0069-0520-02

60mg

Ngenla®
(somatrogon-ghla)
Injection
60 mg/1.2 mL (50 mg/mL)
For Subcutaneous Injection Only

READ ENCLOSED INSTRUCTIONS BEFORE USE

Write the date of first use in the space provided on the
pen label. Discard the pen 28 days after first use, even if
it contains unused medicine.

Before first use: Store refrigerated at 36°F to 46°F (2°C to 8°C)
in the original carton to protect from light. After first use: Store
refrigerated at 36°F to 46°F (2°C to 8°C) between each use for up
to 28 days. Do not freeze or shake. Do not expose to heat.
Store away from direct sunlight. Do not use if it has been frozen.